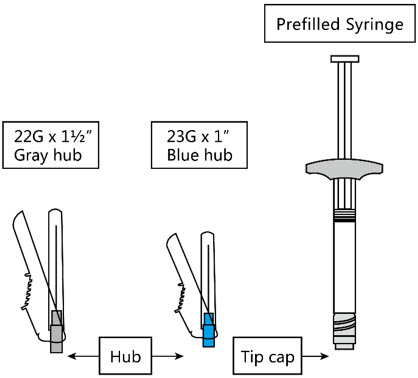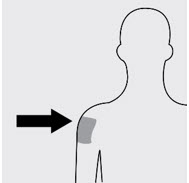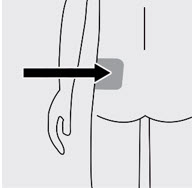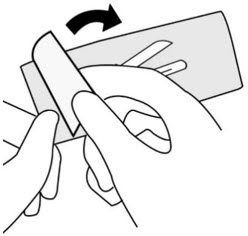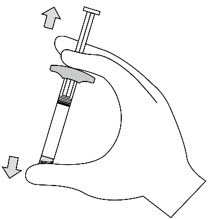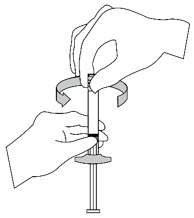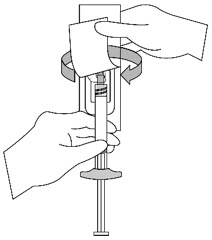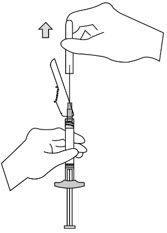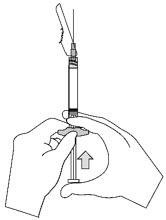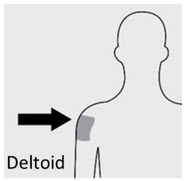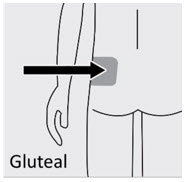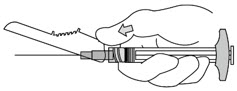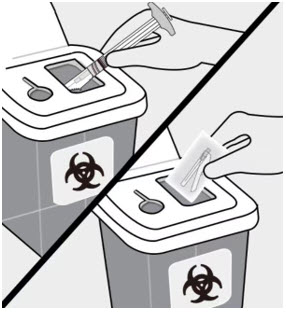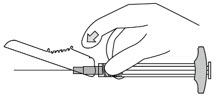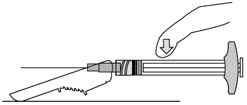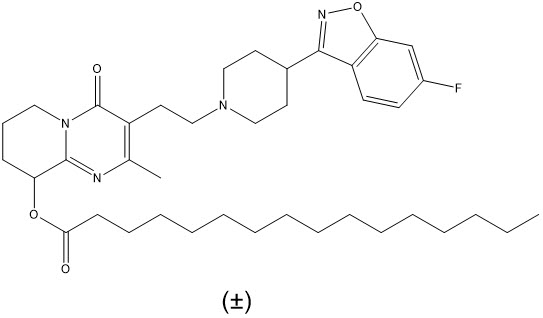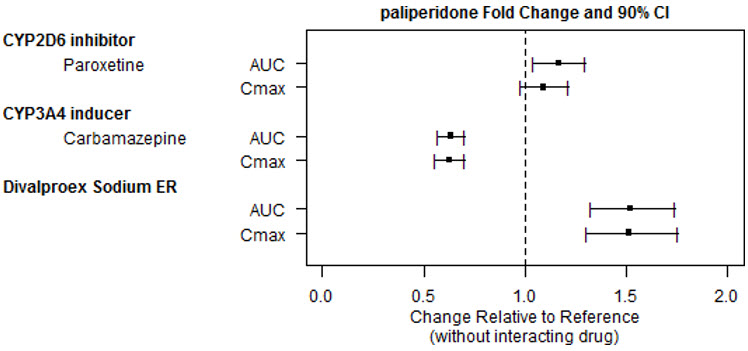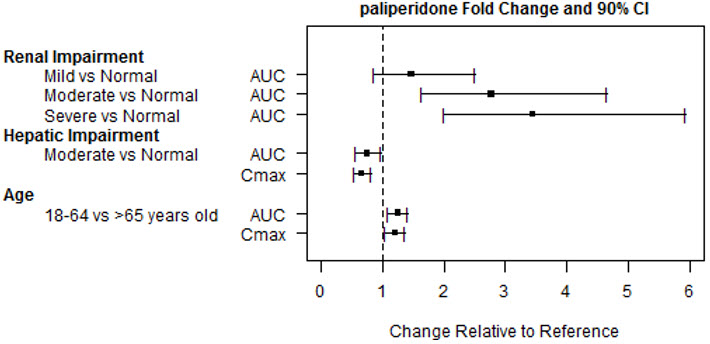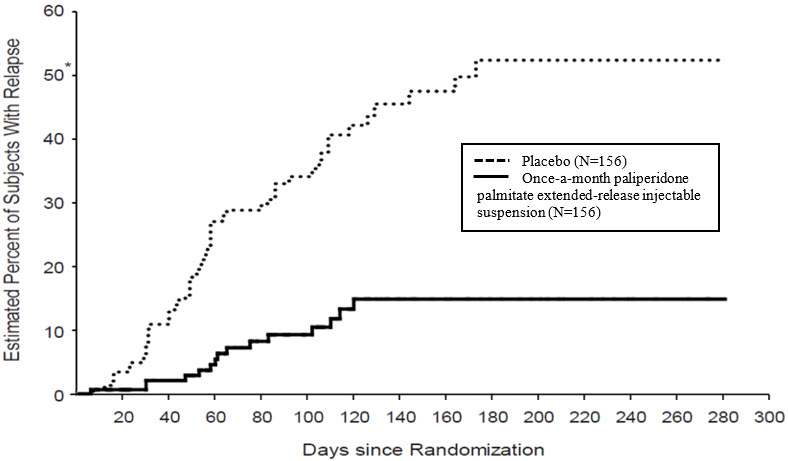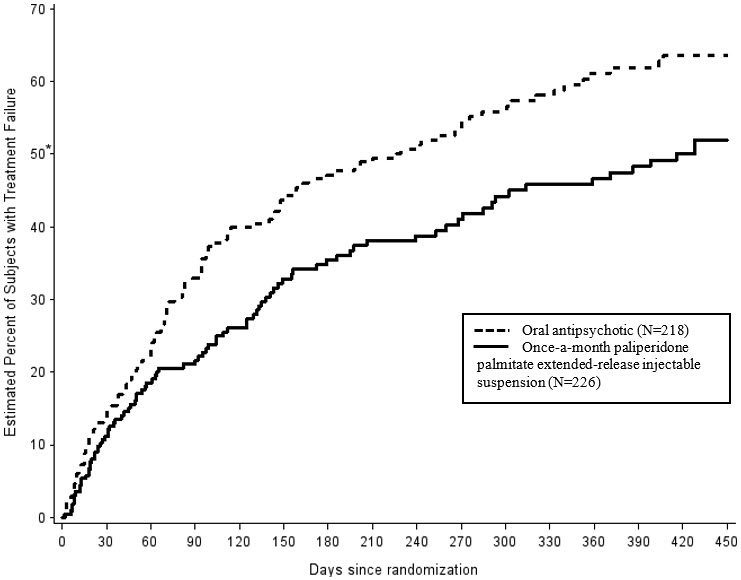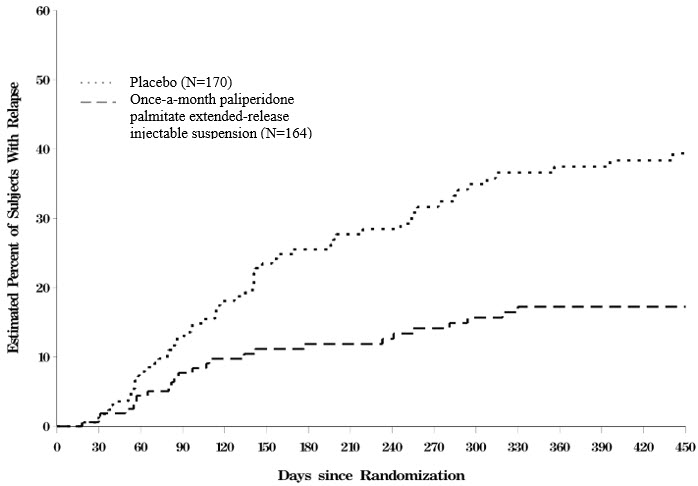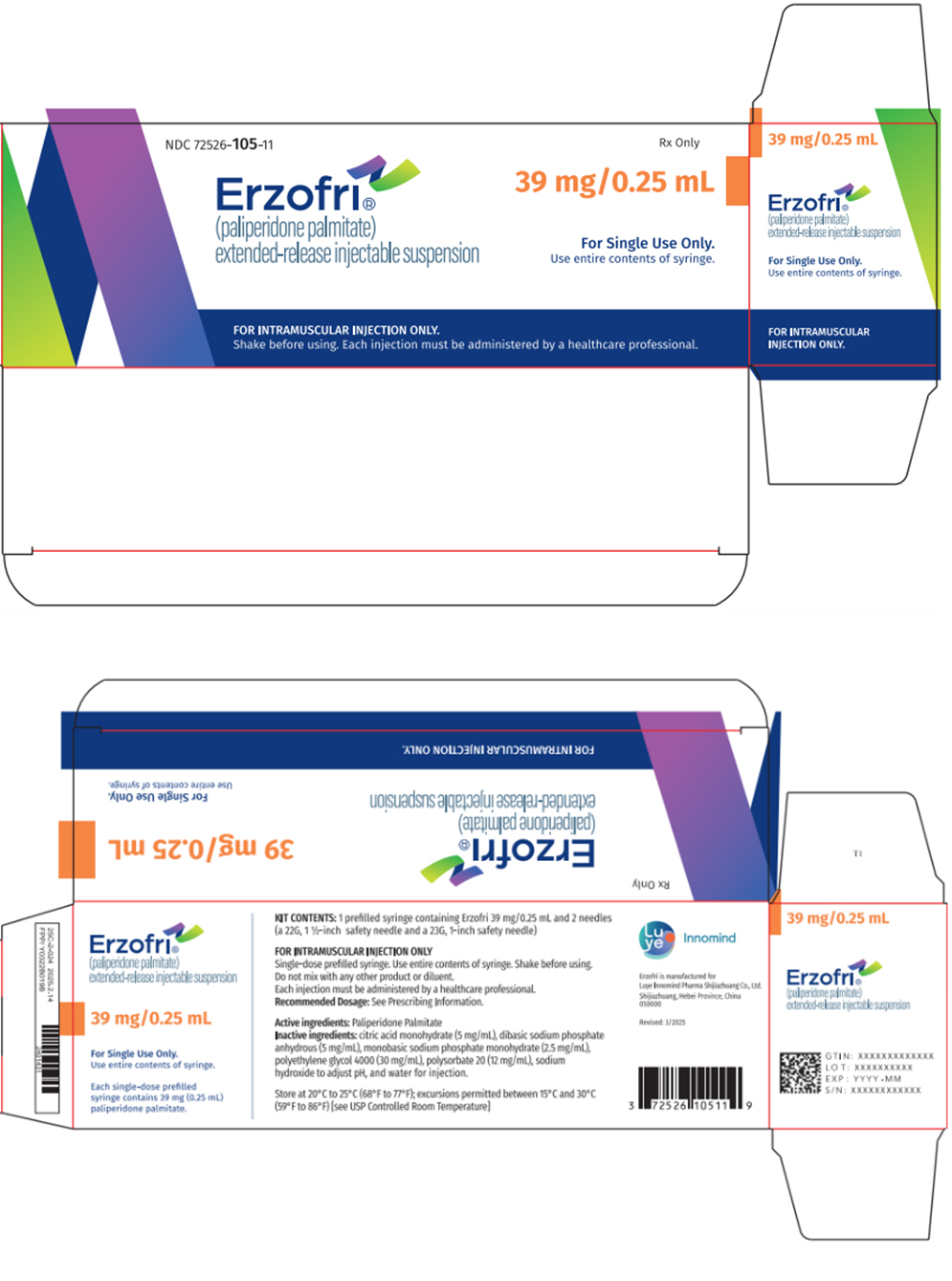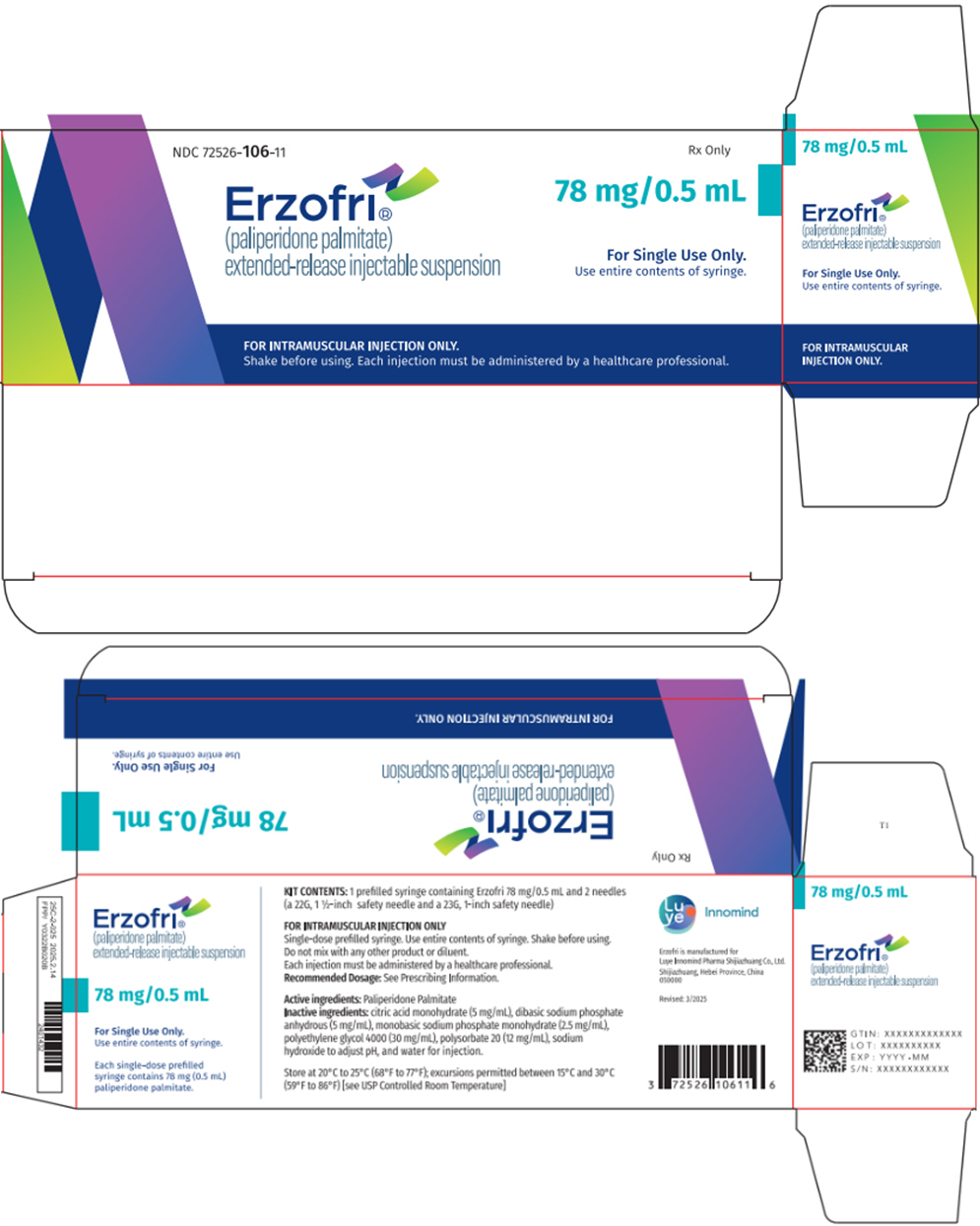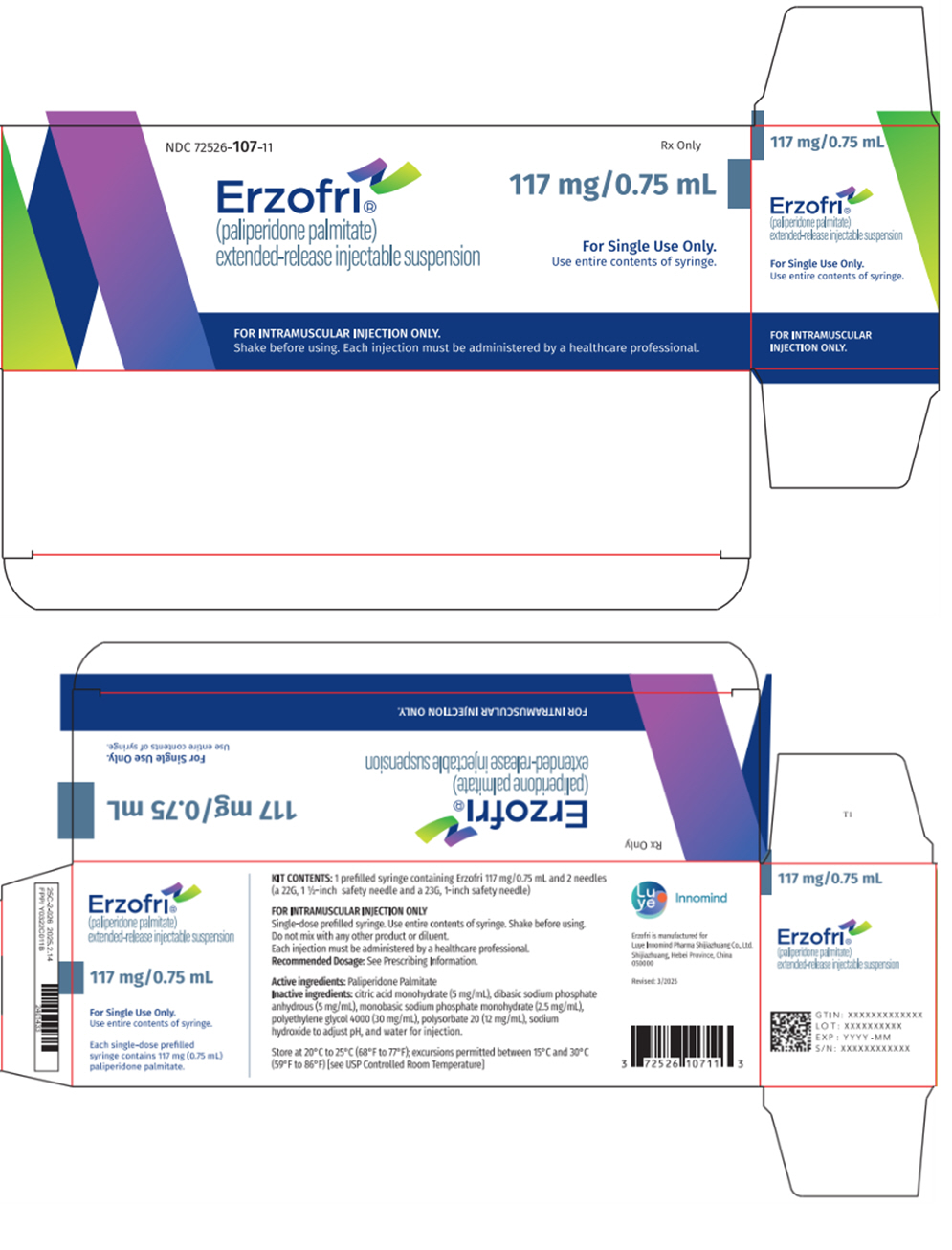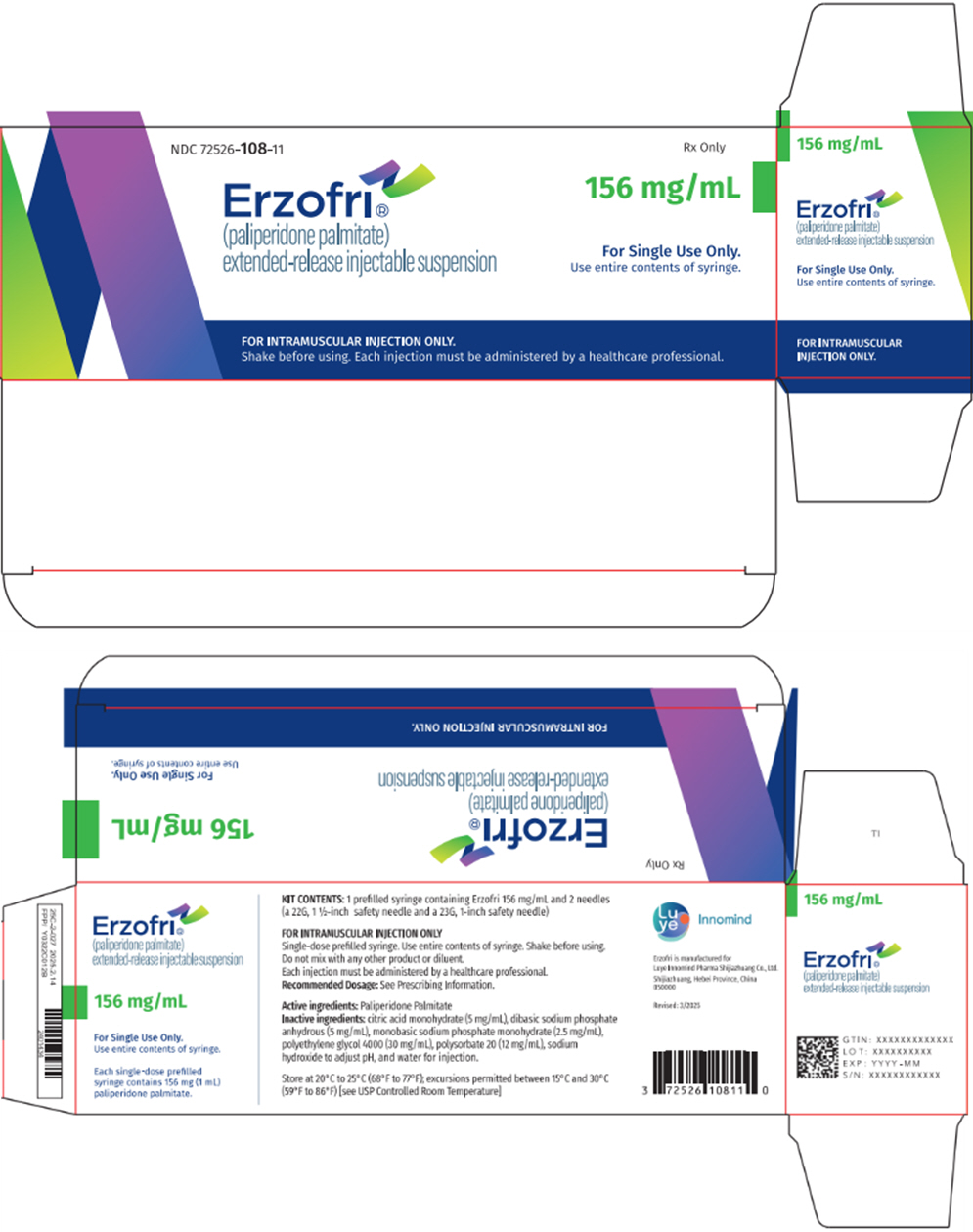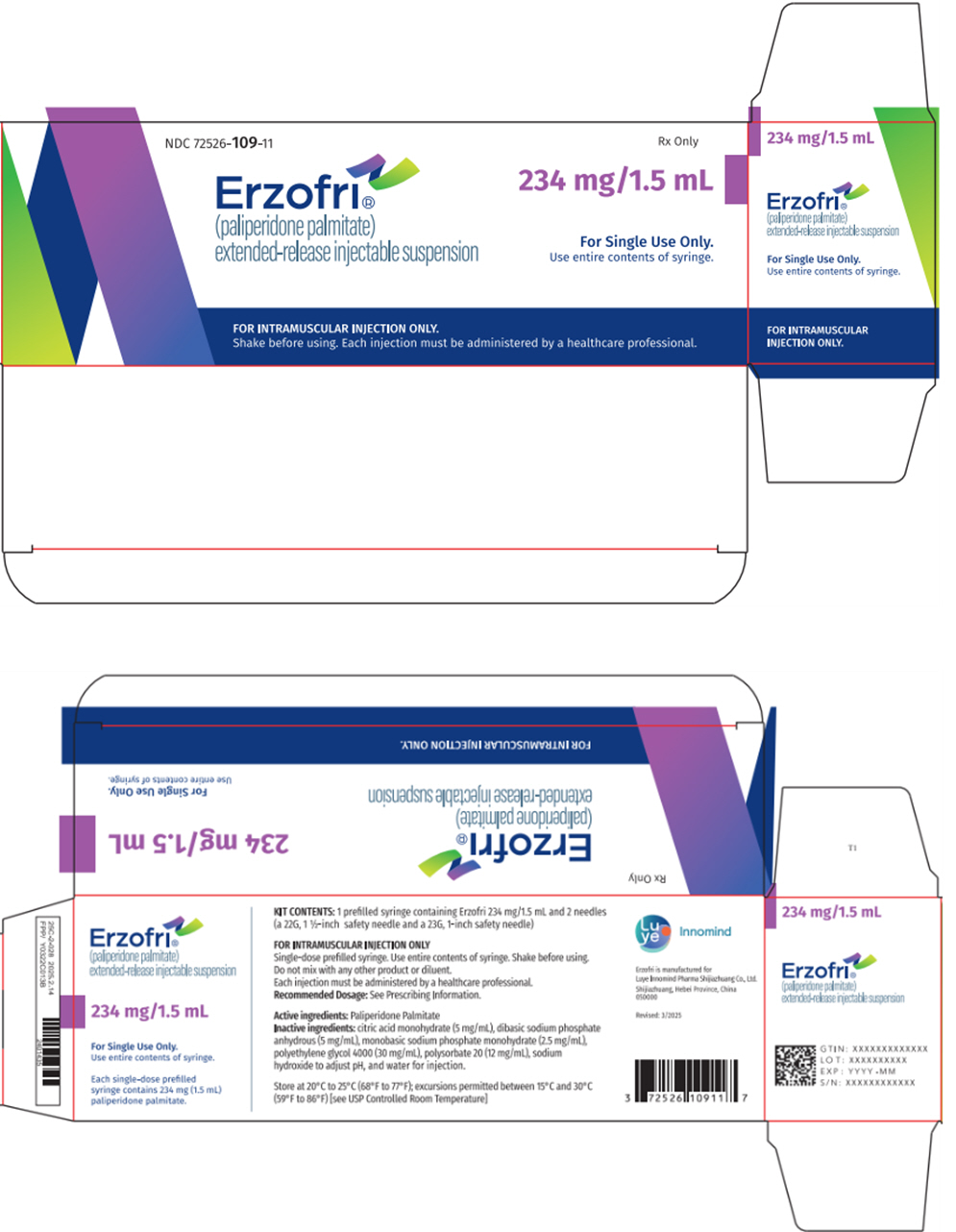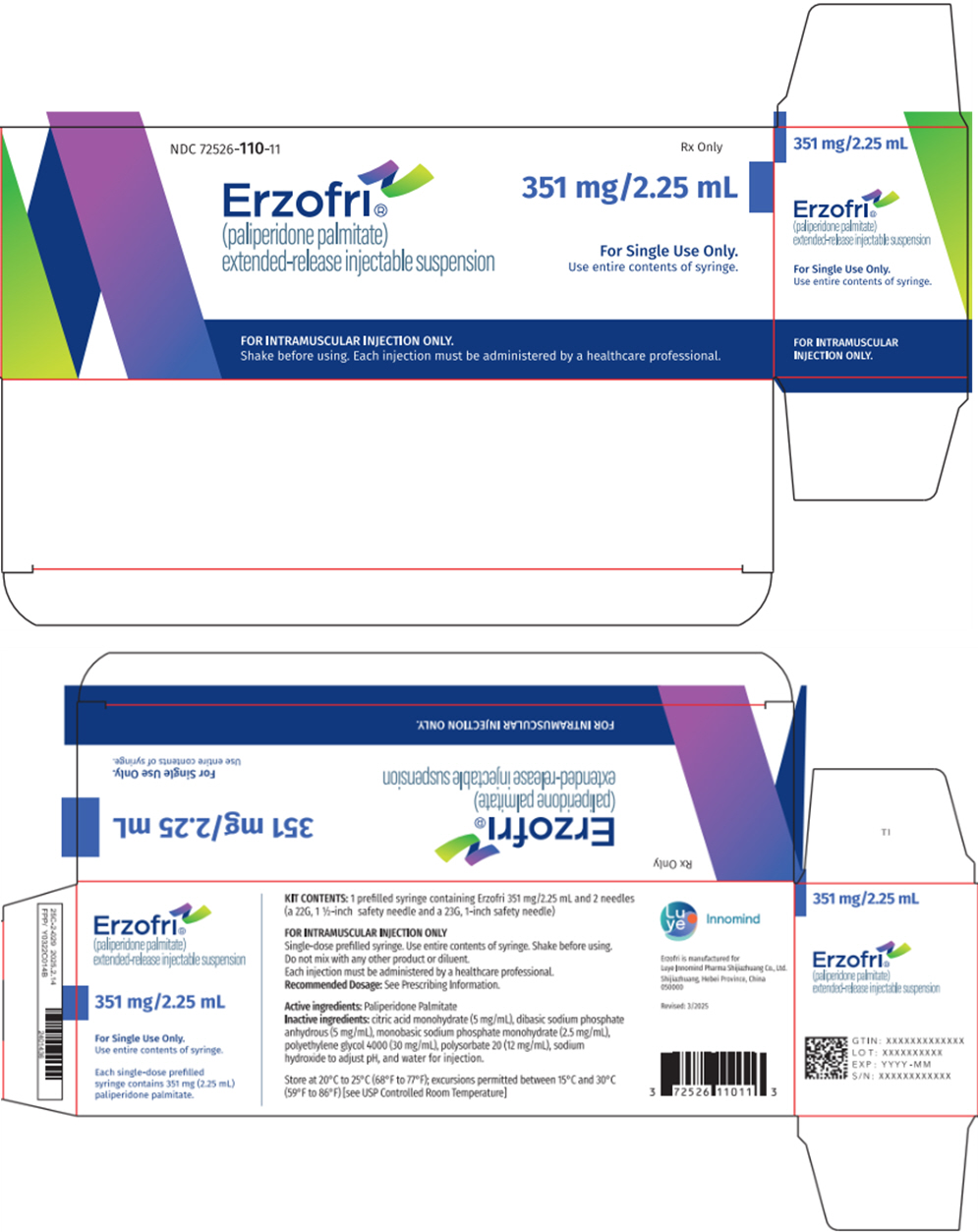 DRUG LABEL: Erzofri extended-release
NDC: 72526-105 | Form: INJECTION
Manufacturer: Shandong Luye Pharmaceutical Co., Ltd.
Category: prescription | Type: HUMAN PRESCRIPTION DRUG LABEL
Date: 20250516

ACTIVE INGREDIENTS: Paliperidone palmitate 39 mg/0.25 mL
INACTIVE INGREDIENTS: citric acid monohydrate; polyethylene glycol 4000; polysorbate 20; sodium hydroxide; sodium phosphate, dibasic, anhydrous; sodium phosphate, monobasic, monohydrate; water

HIGHLIGHTS OF PRESCRIBING INFORMATION

These highlights do not include all the information needed to use ERZOFRI® safely and effectively. See full prescribing information for ERZOFRI®.
ERZOFRI® (paliperidone palmitate) extended-release injectable suspension, for intramuscular use
Initial U.S. Approval: 2006

WARNING: INCREASED MORTALITY IN ELDERLY PATIENTS WITH DEMENTIA- RELATED PSYCHOSIS

See full prescribing information for complete boxed warning.

Elderly patients with dementia-related psychosis treated with antipsychotic drugs are at an increased risk of death. ERZOFRI is not approved for use in patients with dementia-related psychosis. (5.1)

RECENT MAJOR CHANGES

Warnings and Precautions (5.10) | 1/2025

1 INDICATIONS AND USAGE

ERZOFRI is an atypical antipsychotic indicated for:

- Treatment of schizophrenia in adults. (1)
- Treatment of schizoaffective disorder in adults as monotherapy and as an adjunct to mood stabilizers or antidepressants. (1)

2 DOSAGE AND ADMINISTRATION

- For patients naïve to oral or injectable paliperidone, or oral or injectable risperidone, establish tolerability with oral paliperidone or oral risperidone prior to initiating treatment with ERZOFRI. (2.1)
- Each injection must be administered by a healthcare professional. (2.1)
- Initiate ERZOFRI by intramuscular injection in the deltoid muscle. Following the initial dose, monthly doses can be administered in either the gluteal or deltoid muscle. Do not administer by any other route. (2.1)
- Dosage recommendations:

Indication | Initial Dose (deltoid) Day 1 | Monthly Dosage [Administered 4 weeks after the first injection.] (deltoid or gluteal) | Maximum Monthly Dosage
Schizophrenia (2.1) | 351 mg | Monthly Dosage [Administered 4 weeks after the first injection.] (deltoid or gluteal) | Maximum Monthly Dosage | 39 mg to 234 mg [Recommended monthly dosage for treatment of schizophrenia is 117 mg. Some patients may benefit from lower or higher monthly doses within the additional available strengths (39 mg, 78 mg, 156 mg, and 234 mg).] | 234 mg
Schizoaffective disorder (2.1) | 351 mg | 78 mg to 234 mg [Adjust dose based on tolerability and/or efficacy using available strengths. The 39 mg strength was not studied in the long-term schizoaffective disorder study.] | 234 mg

- Missed dose: Refer to the Full Prescribing Information. (2.2)
- Mild renal impairment: Administer 234 mg on treatment Day 1 in the deltoid muscle. Follow with the recommended monthly maintenance dose of 78 mg, administered in the deltoid or gluteal muscle. Adjust monthly maintenance dose based on tolerability and/or efficacy within the strengths of 39 mg, 78 mg, 117 mg, or 156 mg. The maximum monthly dosage is 156 mg for patients with mild renal impairment. (2.4)
- See Full Prescribing Information for important preparation and administration information. (2.7)

3 DOSAGE FORMS AND STRENGTHS

Extended-release injectable suspension: 39 mg/0.25 mL, 78 mg/0.5 mL, 117 mg/0.75 mL, 156 mg/mL, 234 mg/1.5 mL, 351 mg/2.25 mL. (3)

4 CONTRAINDICATIONS

Known hypersensitivity to paliperidone, risperidone, or to any excipients in ERZOFRI. (4)

5 WARNINGS AND PRECAUTIONS

- Cerebrovascular Adverse Reactions, in Elderly Patients with Dementia-Related Psychosis: Increased incidence of cerebrovascular adverse reactions (e.g., stroke, transient ischemic attack, including fatalities). (5.2)
- Neuroleptic Malignant Syndrome: Manage with immediate discontinuation of drug and close monitoring. (5.3)
- QT Prolongation: Avoid use with drugs that also increase QT interval and in patients with risk factors for prolonged QT interval. (5.4)
- Tardive Dyskinesia: Discontinue drug if clinically appropriate. (5.5)
- Metabolic Changes: Monitor for hyperglycemia/diabetes mellitus, dyslipidemia, and weight gain. (5.6)
- Orthostatic Hypotension and Syncope: Use with caution in patients with known cardiovascular or cerebrovascular disease and patients predisposed to hypotension. (5.7)
- Leukopenia, Neutropenia, and Agranulocytosis: Perform complete blood counts (CBC) in patients with history of clinically significant low white blood cell count (WBC) or history of leukopenia or neutropenia. Consider discontinuing ERZOFRI if clinically significant decline in WBC in the absence of other causative factors. (5.9)
- Hyperprolactinemia: Prolactin elevations occur and persist during chronic administration. (5.10)
- Potential for Cognitive and Motor Impairment: Use caution when operating machinery. (5.11)
- Seizures: Use cautiously in patients with a history of seizures or with conditions that lower the seizure threshold. (5.12)

6 ADVERSE REACTIONS

The most common adverse reactions (incidence ≥ 5% and occurring at least twice as often as placebo) were injection site reactions, somnolence/sedation, dizziness, akathisia, and extrapyramidal disorder. (6)

To report SUSPECTED ADVERSE REACTIONS, contact Luye Innomind Pharma Shijiazhuang Co., Ltd. at 1-800-548-9765 or FDA at 1-800-FDA-1088 or www.fda.gov/medwatch.

7 DRUG INTERACTIONS

- Drugs that may cause orthostatic hypotension: An additive effect may occur when co-administered with ERZOFRI. (7.1)
- Strong CYP3A4 and P-glycoprotein (P-gp) inducers: Avoid using a strong inducer of CYP3A4 and/or P-gp during a dosing interval for ERZOFRI. If concomitant use is necessary, consider using paliperidone extended-release tablets. (2.5, 7.1, 12.3)

8 USE IN SPECIFIC POPULATIONS

- Pregnancy: May cause extrapyramidal and/or withdrawal symptoms in neonates with third trimester exposure. (8.1)
- Moderate or severe renal impairment: ERZOFRI is not recommended. (2.4, 8.5)

FULL PRESCRIBING INFORMATION

WARNING: INCREASED MORTALITY IN ELDERLY PATIENTS WITH DEMENTIA- RELATED PSYCHOSIS

Elderly patients with dementia-related psychosis treated with antipsychotic drugs are at an increased risk of death. ERZOFRI is not approved for use in patients with dementia-related psychosis. [see Warnings and Precautions (5.1)].

1 INDICATIONS AND USAGE

ERZOFRI is indicated for the treatment of:

- Schizophrenia in adults.
- Schizoaffective disorder in adults as monotherapy and as an adjunct to mood stabilizers or antidepressants.

2 DOSAGE AND ADMINISTRATION

2.1 Recommended Dosage

For patients who have never taken oral or injectable paliperidone, or oral or injectable risperidone, establish tolerability with oral paliperidone or oral risperidone prior to initiating treatment with ERZOFRI.

ERZOFRI must be administered by a healthcare professional as an intramuscular injection. Do not administer ERZOFRI by any other route. For detailed preparation and administration instructions, see Dosage and Administration (2.7).

See Table 1 for dosage recommendations for ERZOFRI in the treatment of schizophrenia in adults or the treatment of schizoaffective disorder in adults as monotherapy and as an adjunct to mood stabilizers or antidepressants.

The initial dosage of ERZOFRI is 351 mg on treatment Day 1 administered in the deltoid muscle. Following the initial dose, monthly doses can be administered in either the deltoid or gluteal muscle [see Clinical Pharmacology (12.3)].

Table 1: Dosage Recommendations for ERZOFRI
Indication | Initial Dose (deltoid) Day 1 | Monthly Dosage [Administered 4 weeks after the first injection.] (deltoid or gluteal) | Maximum Monthly Dosage
Schizophrenia | 351 mg | Monthly Dosage [Administered 4 weeks after the first injection.] (deltoid or gluteal) | Maximum Monthly Dosage | 39 mg to 234 mg [The recommended monthly dosage for treatment of schizophrenia is 117 mg. Some patients may benefit from lower or higher monthly doses within the additional available strengths (39 mg, 78 mg, 156 mg, and 234 mg).] | 234 mg
Schizoaffective disorder | 351 mg | 78 mg to 234 mg [Adjust dose based on tolerability and/or efficacy using available strengths. The 39 mg strength was not studied in the long-term schizoaffective disorder study.] | 234 mg

Adjust dosage monthly depending on clinical response and tolerability. When making dose adjustments, the pharmacokinetic profile of ERZOFRI should be considered [see Clinical Pharmacology (12.3)], as the full effect of the dose adjustment may not be apparent for several months.

2.2 Missed Doses

Dosing Window

To avoid a missed monthly dose, patients may be given the injection up to 7 days before or after the monthly time point.

Missed Dose

If a dose of ERZOFRI is missed, follow the dosing instructions provided in Table 2.

Table 2: Management of a Missed Dose of ERZOFRI
TIMING OF MISSED DOSE | DOSING
4 to 6 weeks since last injection | Resume regular monthly dosing as soon as possible at the patient's previously stabilized dose, followed by injections at monthly intervals.
More than 6 weeks to 6 months since last injection | Resume the same dose the patient was previously stabilized on (unless the patient was stabilized on a dose of 234 mg, then the first 2 injections should each be 156 mg) in the following manner:; 1. Administer a deltoid injection as soon as possible. 2. Administer a second deltoid injection 1 week later at the same dose. 3. Thereafter, resume administering the previously stabilized dose in the deltoid or gluteal muscle 1 month after the second injection.
More than 6 months since last injection | Restart dosing with recommended initiation (see Section 2.1, Table 1):; 1. Administer a 351 mg deltoid injection on Day 1. 2. Thereafter, resume administering the previously stabilized dose in the deltoid or gluteal muscle 1 month after the initial injection.

2.3 Use with Risperidone or with Oral Paliperidone

Paliperidone is the major active metabolite of risperidone. Exercise caution if ERZOFRI is co-administered with risperidone or with oral paliperidone for extended periods of time. Safety data involving concomitant use of ERZOFRI with other antipsychotics is limited.

2.4 Dosage Recommendations for Patients with Renal Impairment

For patients with mild renal impairment (creatinine clearance ≥ 50 mL/min to < 80 mL/min [Cockcroft-Gault Formula]), initiate ERZOFRI with a dose of 234 mg on treatment Day 1 in the deltoid muscle. Follow with the recommended monthly dosage of 78 mg, administered in either the deltoid or gluteal muscle. Adjust monthly dosage based on tolerability and/or response within the strengths of 39 mg, 78 mg, 117 mg, or 156 mg. The maximum monthly dosage is 156 mg for patients with mild renal impairment [see Use in Specific Populations (8.6) and Clinical Pharmacology (12.3)].

ERZOFRI is not recommended in patients with moderate or severe renal impairment (creatinine clearance < 50 mL/min) [see Use in Specific Populations (8.6) and Clinical Pharmacology (12.3)].

2.5 Dosage Modifications for Concomitant Use with Strong CYP3A4 Inducers and/or P-gp Inducers

Avoid using a strong inducer of CYP3A4 and/or P-gp during the one-month dosing interval for ERZOFRI, if possible. If administering a strong inducer is necessary, consider managing the patient using paliperidone extended-release tablets [see Drug Interactions (7.1) and Clinical Pharmacology (12.3)].

2.6 Switching from Other Antipsychotics

There are no systematically collected data to specifically address switching patients with schizophrenia or schizoaffective disorder from other antipsychotics to ERZOFRI or concerning concomitant administration with other antipsychotics.

Switching from Oral Antipsychotics

Previous oral antipsychotics can be gradually discontinued at the time of initiation of treatment with ERZOFRI. The recommended initial dosage of ERZOFRI is 351 mg on treatment Day 1, administered in the deltoid muscle [see Dosage and Administration (2.1)]. See Table 3 for subsequent monthly dosage recommendations for ERZOFRI in patients switching from oral extended-release paliperidone tablets.

Table 3: Dosage Recommendations Following Initial Dose of ERZOFRI in Patients Switching from Oral Extended-Release Paliperidone Tablets
 | Paliperidone Extended-Release Tablet | ERZOFRI
Dosing Frequency | Once Daily | Once every 4 weeks
 | 12 mg | 234 mg
Dose | 9 mg | 156 mg
 | 6 mg | 117 mg
 | 3 mg | 39 mg to 78 mg

Switching from Long-Acting Injectable Antipsychotics

When switching patients currently at steady-state on a long-acting injectable antipsychotic, initiate ERZOFRI therapy in place of the next scheduled injection.

Continue ERZOFRI at monthly intervals. The initial dosing regimen as described in Section 2.1 is not required. See Table 1 for recommended monthly dosing. Based on previous clinical response and tolerability, some patients may benefit from lower or higher doses within the available strengths (39 mg, 78 mg, 117 mg, 156 mg, and 234 mg).

If ERZOFRI is discontinued, its pharmacokinetic characteristics must be considered. As recommended with other antipsychotic medications, the need for continuing existing extrapyramidal symptoms (EPS) medication should be re-evaluated periodically.

2.7 Preparation and Administration Instructions

- To be prepared and administered by a healthcare professional only.
- Read the instructions for preparation and administration below for preparation and administration considerations.
- For deltoid or gluteal intramuscular injection only. Do not inject by any other route.
- Administer the initial dosage of ERZOFRI in the deltoid muscle. Subsequent monthly dosages may be administered in the deltoid or gluteal muscle.
- As a universal precaution, always wear gloves.
- Do not substitute any component of the drug kit.

The kit contains a prefilled syringe and 2 safety needles (a 1 ½-inch 22 gauge needle and a 1-inch 23 gauge needle).

ERZOFRI is for single use only.

Step 1. Select Needle

For Deltoid injection | For Gluteal injection
If the patient weighs less than 90 kg, use the 1-inch 23 gauge needle (needle with blue colored hub) | Use the 1 ½-inch 22 gauge needle (needle with gray colored hub) regardless of patient's weight
If the patient weighs 90 kg or more, use the 1 ½-inch 22 gauge needle (needle with gray colored hub) | Use the 1 ½-inch 22 gauge needle (needle with gray colored hub) regardless of patient's weight

Step 2. Prepare for Injection

a. Open needle pouch

b. Shake vigorously for at least 10 seconds

c. Remove cap

First, peel the safety needle pouch half way open. Place on a clean surface.

Shake the syringe vigorously for a minimum of 10 seconds to ensure a homogeneous suspension.

While holding the syringe upright, remove the rubber tip cap with an easy counterclockwise twisting motion. Do not touch syringe tip.

d. Attach needle

e. Remove needle sheath

f. Remove air bubbles

Grasp the needle sheath using the plastic peel pouch. Attach the safety needle to the luer connection of the syringe with an easy clockwise twisting motion.
Do not remove the pouch until the syringe and needle are securely attached.

Pull the needle sheath away from the needle with a straight pull. Do not twist the sheath as the needle may be loosened from the syringe.

Bring the syringe with the attached needle in upright position to de-aerate. De-aerate the syringe by moving the plunger rod carefully forward.

Step 3. Inject

Inject the entire contents intramuscularly slowly, deep into the selected deltoid or gluteal muscle of the patient. Do not administer by any other route.

Step 4. After Injection

Secure Needle | Dispose properly
a | Dispose of the syringe and unused needle in an approved sharps container.
 | Dispose of the syringe and unused needle in an approved sharps container.
b | Dispose of the syringe and unused needle in an approved sharps container.
 | Dispose of the syringe and unused needle in an approved sharps container.
c | Dispose of the syringe and unused needle in an approved sharps container.
 | Dispose of the syringe and unused needle in an approved sharps container.
After the injection is complete, use either thumb or finger of one hand (a, b) or a flat surface (c) to activate the needle protection system. The needle protection system is fully activated when a 'click' is heard. | Dispose of the syringe and unused needle in an approved sharps container.

3 DOSAGE FORMS AND STRENGTHS

Extended-release injectable suspension: white to off-white aqueous suspension available in dose strengths of 39 mg/0.25 mL, 78 mg/0.5 mL, 117 mg/0.75 mL, 156 mg/mL, 234 mg/1.5 mL, and 351 mg/2.25 mL paliperidone palmitate.

Each strength is provided as a kit, which includes: one single-dose prefilled syringe and 2 safety needles (a 1 ½-inch 22 gauge needle and a 1-inch 23 gauge needle).

4 CONTRAINDICATIONS

ERZOFRI is contraindicated in patients with a known hypersensitivity to either paliperidone or risperidone, or to any of the excipients in the ERZOFRI formulation. Hypersensitivity reactions, including anaphylactic reactions and angioedema, have been reported in patients treated with risperidone and in patients treated with paliperidone [see Adverse Reactions (6.1, 6.2)].

5 WARNINGS AND PRECAUTIONS

5.1 Increased Mortality in Elderly Patients with Dementia-Related Psychosis

Elderly patients with dementia-related psychosis treated with antipsychotic drugs are at an increased risk of death. Analyses of 17 placebo-controlled trials (modal duration of 10 weeks), largely in patients taking atypical antipsychotic drugs, revealed a risk of death in drug-treated patients of between 1.6 to 1.7 times the risk of death in placebo-treated patients. Over the course of a typical 10-week controlled trial, the rate of death in drug-treated patients was about 4.5%, compared to a rate of about 2.6% in the placebo group.

Although the causes of death were varied, most of the deaths appeared to be either cardiovascular (e.g., heart failure, sudden death) or infectious (e.g., pneumonia) in nature. Observational studies suggest that, similar to atypical antipsychotic drugs, treatment with conventional antipsychotic drugs may increase mortality. The extent to which the findings of increased mortality in observational studies may be attributed to the antipsychotic drug as opposed to some characteristic(s) of the patients is not clear.

ERZOFRI is not approved for the treatment of patients with dementia-related psychosis [see Boxed Warning and Warnings and Precautions (5.2)].

5.2 Cerebrovascular Adverse Reactions, Including Stroke, in Elderly Patients with Dementia-Related Psychosis

In placebo-controlled trials with risperidone, aripiprazole, and olanzapine in elderly subjects with dementia, there was a higher incidence of cerebrovascular adverse reactions (cerebrovascular accidents and transient ischemic attacks) including fatalities compared to placebo-treated subjects. No studies have been conducted with oral paliperidone, 1-month or 3-month paliperidone palmitate extended-release injectable suspensions, or ERZOFRI, in elderly patients with dementia. ERZOFRI is not approved for the treatment of patients with dementia-related psychosis [see Boxed Warning and Warnings and Precautions (5.1)].

5.3 Neuroleptic Malignant Syndrome

Neuroleptic Malignant Syndrome (NMS), a potentially fatal symptom complex, has been reported in association with antipsychotic drugs, including paliperidone.

Clinical manifestations of NMS are hyperpyrexia, muscle rigidity, altered mental status including delirium, and autonomic instability (irregular pulse or blood pressure, tachycardia, diaphoresis, and cardiac dysrhythmia). Additional signs may include elevated creatine phosphokinase, myoglobinuria (rhabdomyolysis), and acute renal failure.

If NMS is suspected, immediately discontinue ERZOFRI and provide symptomatic treatment and monitoring.

5.4 QT Prolongation

Paliperidone causes a modest increase in the corrected QT (QTc) interval. The use of paliperidone should be avoided in combination with other drugs that are known to prolong QTc including Class 1A (e.g., quinidine, procainamide) or Class III (e.g., amiodarone, sotalol) antiarrhythmic medications, antipsychotic medications (e.g., chlorpromazine, thioridazine), antibiotics (e.g., gatifloxacin, moxifloxacin), or any other class of medications known to prolong the QTc interval. Paliperidone should also be avoided in patients with congenital long QT syndrome and in patients with a history of cardiac arrhythmias.

Certain circumstances may increase the risk of the occurrence of Torsades de pointes and/or sudden death in association with the use of drugs that prolong the QTc interval, including (1) bradycardia; (2) hypokalemia or hypomagnesemia; (3) concomitant use of other drugs that prolong the QTc interval; and (4) presence of congenital prolongation of the QT interval.

The effects of oral paliperidone on the QT interval were evaluated in a double-blind, active-controlled (moxifloxacin 400 mg single dose), multicenter QT study in adults with schizophrenia and schizoaffective disorder, and in three placebo- and active-controlled 6-week, fixed-dose efficacy trials in adults with schizophrenia.

In the QT study (n=141) of oral paliperidone, the 8 mg dose of immediate-release oral paliperidone (n=50) showed a mean placebo-subtracted increase from baseline in QTcLD (QT interval corrected for heart rate using the population specified linear derived method) of 12.3 msec (90% CI: 8.9; 15.6) on Day 8 at 1.5 hours post-dose. The mean steady-state peak plasma concentration for this 8 mg oral dose of immediate release paliperidone (Cmax ss = 113 ng/mL) was more than 2-fold the exposure observed with the maximum recommended 234 mg maintenance dose of another once-a-month paliperidone extended-release injectable suspension administered in the deltoid muscle (predicted median Cmax-ss = 50 ng/mL). In this same study, a 4 mg dose of the immediate-release oral formulation of paliperidone, for which Cmax-ss = 35 ng/mL, showed an increased placebo-subtracted QTcLD of 6.8 msec (90% CI: 3.6; 10.1) on Day 2 at 1.5 hours post-dose.

In the three fixed-dose efficacy studies of oral paliperidone extended release in subjects with schizophrenia, electrocardiogram (ECG) measurements taken at various time points showed only one subject in the oral paliperidone 12 mg group had a change exceeding 60 msec at one time- point on Day 6 (increase of 62 msec).

In the four fixed-dose efficacy studies of another once-a-month paliperidone palmitate extended-release injectable suspension in subjects with schizophrenia and in the long-term study in subjects with schizoaffective disorder, no subject experienced a change in QTcLD exceeding 60 msec and no subject had a QTcLD value of > 500 msec at any time point. In the maintenance study in subjects with schizophrenia, no subject had a QTcLD change > 60 msec, and one subject had a QTcLD value of 507 msec (Bazett's QT corrected interval [QTcB] value of 483 msec); this latter subject also had a heart rate of 45 beats per minute.

5.5 Tardive Dyskinesia

Tardive dyskinesia, a syndrome consisting of potentially irreversible, involuntary, dyskinetic movements, may develop in patients treated with antipsychotic drugs. Although the prevalence of the syndrome appears to be highest among the elderly, especially elderly women, it is impossible to predict which patients will develop the syndrome. Whether antipsychotic drug products differ in their potential to cause tardive dyskinesia is unknown.

The risk of developing tardive dyskinesia and the likelihood that it will become irreversible appear to increase with the duration of treatment and the cumulative dose. The syndrome can develop after relatively brief treatment periods, even at low doses. It may also occur after discontinuation of treatment.

Tardive dyskinesia may remit, partially or completely, if antipsychotic treatment is discontinued. Antipsychotic treatment itself may suppress (or partially suppress) the signs and symptoms of the syndrome and may thus mask the underlying process. The effect that symptomatic suppression has upon the long-term course of the syndrome is unknown.

Given these considerations, ERZOFRI should be prescribed in a manner that is most likely to minimize the occurrence of tardive dyskinesia. Chronic antipsychotic treatment should generally be reserved for patients: (1) who suffer from a chronic illness that is known to respond to antipsychotic drugs and (2) for whom alternative, equally effective, but potentially less harmful treatments are not available or appropriate. In patients who do require chronic treatment, use the lowest dose and the shortest duration of treatment producing a satisfactory clinical response. Periodically reassess the need for continued treatment.

If signs and symptoms of tardive dyskinesia appear in a patient on ERZOFRI, drug discontinuation should be considered. However, some patients may require treatment with ERZOFRI despite the presence of the syndrome.

5.6 Metabolic Changes

Atypical antipsychotic drugs have been associated with metabolic changes that may increase cardiovascular/cerebrovascular risk. These metabolic changes include hyperglycemia, dyslipidemia, and body weight gain. While all of the drugs in the class have been shown to produce some metabolic changes, each drug has its own specific risk profile.

Hyperglycemia and Diabetes Mellitus

Hyperglycemia and diabetes mellitus, in some cases extreme and associated with ketoacidosis or hyperosmolar coma or death, have been reported in patients treated with all atypical antipsychotics. These cases were, for the most part, seen in post-marketing clinical use and epidemiologic studies, not in clinical trials. Hyperglycemia and diabetes have been reported in trial subjects treated with another once-a-month paliperidone palmitate extended-release injectable suspension (also referred to as "PP1M" in this section). Assessment of the relationship between atypical antipsychotic use and glucose abnormalities is complicated by the possibility of an increased background risk of diabetes mellitus in patients with schizophrenia and the increasing incidence of diabetes mellitus in the general population. Given these confounders, the relationship between atypical antipsychotic use and hyperglycemia-related adverse events is not completely understood. However, epidemiological studies suggest an increased risk of hyperglycemia-related adverse reactions in patients treated with the atypical antipsychotics.

Patients with an established diagnosis of diabetes mellitus who are started on atypical antipsychotics should be monitored regularly for worsening of glucose control. Patients with risk factors for diabetes mellitus (e.g., obesity, family history of diabetes) who are starting treatment with atypical antipsychotics should undergo fasting blood glucose testing at the beginning of treatment and periodically during treatment. Any patient treated with atypical antipsychotics should be monitored for symptoms of hyperglycemia including polydipsia, polyuria, polyphagia, and weakness. Patients who develop symptoms of hyperglycemia during treatment with atypical antipsychotics should undergo fasting blood glucose testing. In some cases, hyperglycemia has resolved when the atypical antipsychotic was discontinued; however, some patients required continuation of anti-diabetic treatment despite discontinuation of the suspect drug.

Pooled data from the four placebo-controlled (one 9-week and three 13-week), fixed-dose studies of another PP1M in subjects with schizophrenia are presented in Table 4.

Table 4: Change in Fasting Glucose from Four Placebo-Controlled, 9- to 13-Week, Fixed-Dose Studies in Subjects with Schizophrenia
 |  | Once-a-Month Paliperidone Palmitate Extended-Release Injectable Suspension
 | Placebo | 39 mg | 78 mg | 156 mg | 234/39 mg [Initial deltoid injection of 234 mg followed by either 39 mg, 156 mg, or 234 mg every 4 weeks by deltoid or gluteal injection. Other dose groups (39 mg, 78 mg, and 156 mg) are from studies involving only gluteal injection. [see Clinical Studies (14.1)].] | 234/156 mg | 234/234 mg
Mean change from baseline (mg/dL)
 | n=367 | n=86 | n-244 | n=238 | n=110 | n=126 | n=115
Serum Glucose Change from baseline | -1.3 | 1.3 | 3.5 | 0.1 | 3.4 | 1.8 | -0.2
Proportion of Patients with Shifts
Serum Glucose Normal to High | 4.6% | 6.3% | 6.4% | 3.9% | 2.5% | 7.0% | 6.6%
(<100 mg/dL to ≥126 mg/dL) | (11/241) | (4/64) | (11/173) | (6/154) | (2/79) | (6/86) | (5/76)

In a long-term open-label pharmacokinetic and safety study in subjects with schizophrenia in which the highest maintenance dose available (234 mg) was evaluated, another PP1M was associated with a mean change in glucose of -0.4 mg/dL at Week 29 (n=109) and +6.8 mg/dL at Week 53 (n=100).

During the initial 25-week open-label period of a long-term study in subjects with schizoaffective disorder, another PP1M was associated with mean change in glucose of +5.3 mg/dL (n=518). At the endpoint of the subsequent 15-month double-blind period of the study, the PP1M was associated with a mean change in glucose of +0.3 mg/dL (n=131) compared with a mean change of +4.0 mg/dL in the placebo group (n=120).

Dyslipidemia

Undesirable alterations in lipids have been observed in patients treated with atypical antipsychotics.

Pooled data from the four placebo-controlled (one 9-week and three 13-week), fixed-dose studies of another PP1M in subjects with schizophrenia are presented in Table 5.

Table 5: Change in Fasting Lipids from Four Placebo-Controlled, 9- to 13-Week, Fixed-Dose Studies in Subjects with Schizophrenia
 |  | Once-a-Month Paliperidone Palmitate Extended-Release Injectable Suspension
 | Placebo | 39 mg | 78 mg | 156 mg | 234/39 mg [Initial deltoid injection of 234 mg followed by either 39 mg, 156 mg, or 234 mg every 4 weeks by deltoid or gluteal injection. Other dose groups (39 mg, 78 mg, and 156 mg) are from studies involving only gluteal injection. [see Clinical Studies (14.1)].] | 234/156 mg | 234/234 mg
Mean change from baseline (mg/dL)
Cholesterol | n=366 | n=89 | n=244 | n=232 | n=105 | n=119 | n=120
Change from baseline | -6.6 | -6.4 | -5.8 | -7.1 | -0.9 | -4.2 | 9.4
LDL | n=275 | n=80 | n=164 | n=141 | n=104 | n=117 | n=108
Change from baseline | -6.0 | -4.8 | -5.6 | -4.8 | 0.9 | -2.4 | 5.2
HDL | n=286 | n=89 | n=165 | n=150 | n=105 | n=118 | n=115
Change from baseline | 0.7 | 2.1 | 0.6 | 0.3 | 1.5 | 1.1 | 0.0
Triglycerides | n=366 | n=89 | n=244 | n=232 | n=105 | n=119 | n=120
Change from baseline | -16.7 | 7.6 | -9.0 | -11.5 | -14.1 | -20.0 | 11.9
Proportion of Patients with Shifts
Cholesterol Normal to High | 3.2% | 2.0% | 2.0% | 2.1% | 0% | 3.1% | 7.1%
(<200 mg/dL to ≥240 mg/dL) | (7/222) | (1/51) | (3/147) | (3/141) | (0/69) | (2/65) | (6/84)
LDL Normal to High | 1.1% | 0% | 0% | 0% | 0% (0/41) | 0% | 0%
(<100 mg/dL to ≥160 mg/dL) | (1/95) | (0/29) | (0/67) | (0/46) | 0% (0/41) | (0/37) | (0/44)
HDL Normal to Low | 13.8% | 14.8% | 9.6% | 14.2% | 12.7% | 10.5% | 16.0%
(≥40 mg/dL to <40 mg/dL | (28/203) | (9/61) | (11/115) | (15/106) | (9/71) | (8/76) | (13/81)
Triglycerides Normal to High | 3.6% | 6.1% | 9.2% | 7.2% | 1.3% | 3.7% | 10.7%
(<150 mg/dL to ≥200 mg/dL) | (8/221) | (3/49) | (14/153) | (10/139) | (1/79) | (3/82) | (9/84)

In a long-term open-label pharmacokinetic and safety study in subjects with schizophrenia in which the highest maintenance dose available (234 mg) was evaluated, the mean changes from baseline in lipid values are presented in Table 6.

Table 6: Change in Fasting Lipids from Long-term Open-label Pharmacokinetic and Safety Study in Subjects with Schizophrenia
 | Once-a-Month Paliperidone Palmitate Extended-Release Injectable Suspension 234 mg
 | Week 29 | Week 53
 | Mean change from baseline (mg/dL)
Cholesterol | n=112 | n=100
Change from baseline | -1.2 | 0.1
LDL | n=107 | n=89
Change from baseline | -2.7 | -2.3
HDL | n=112 | n=98
Change from baseline | -0.8 | -2.6
Triglycerides | n=112 | n=100
Change from baseline | 16.2 | 37.4

The mean changes from baseline in lipid values during the initial 25-week open-label period and at the endpoint of the subsequent 15-month double-blind period in a long-term study of another PP1M in subjects with schizoaffective disorder are presented in Table 7.

Table 7: Change in Fasting Lipids from an Open-Label and Double-Blind Periods of a Long-Term Study in Subjects with Schizoaffective Disorder
 | Open-Label Period | Double-Blind Period
 | Once-a-Month Paliperidone Palmitate Extended-Release Injectable Suspension | Placebo | Once-a-Month Paliperidone Palmitate Extended-Release Injectable Suspension
 | Mean change from baseline (mg/dL)
Cholesterol | n=198 | n=119 | n=132
Change from baseline | -3.9 | -4.2 | 2.3
LDL | n=198 | n=117 | n=130
Change from baseline | -2.7 | -2.8 | 5.9
HDL | n=198 | n=119 | n=131
Change from baseline | -2.7 | -0.9 | -0.7
Triglyceride | n=198 | n=119 | n=132
Change from baseline | 7.0 | 2.5 | -12.3

Weight Gain

Weight gain has been observed with atypical antipsychotic use. Clinical monitoring of weight is recommended.

Data on mean changes in body weight and the proportion of subjects meeting a weight gain criterion of ≥ 7% of body weight from the four placebo-controlled (one 9-week and three 13-week), fixed-dose studies of another PP1M in subjects with schizophrenia are presented in Table 8.

Table 8: Mean Change in Body Weight (kg) and the Proportion of Subjects with ≥ 7% Gain in Body Weight from Four Placebo-Controlled, 9- to 13-Week, Fixed-Dose Studies in Subjects with Schizophrenia
 | Once-a-Month Paliperidone Palmitate Extended-Release Injectable Suspension
 | Placebo n=451 | 39 mg n=116 | 78 mg n=280 | 156 mg n=267 | 234/39 mg [Initial deltoid injection of 234 mg followed by either 39 mg, 156 mg, or 234 mg every 4 weeks by deltoid or gluteal injection. Other dose groups (39 mg, 78 mg, and 156 mg) are from studies involving only gluteal injection. [see Clinical Studies (14.1)].] n=137 | 234/156 mg n=144 | 234/234 mg n=145
Weight (kg) Change from baseline | -0.4 | 0.4 | 0.8 | 1.4 | 0.4 | 0.7 | 1.4
Weight Gain ≥ 7% increase from baseline | 3.3 % | 6.0% | 8.9% | 9.0% | 5.8% | 8.3% | 13.1 %

In a long-term open-label pharmacokinetic and safety study in which the highest maintenance dose available (234 mg) was evaluated, another PP1M was associated with a mean change in weight of +2.4 kg at Week 29 (n=134) and +4.3 kg at Week 53 (n=113).

During the initial 25-week open-label period of a long-term study in subjects with schizoaffective disorder, another PP1M was associated with a mean change in weight of +2.2 kg and 18.4% of subjects had an increase in body weight of ≥ 7% (n=653). At the endpoint of the subsequent 15-month double-blind period of the study, the PP1M was associated with a mean change in weight of -0.2 kg and 13.0% of subjects had an increase in body weight of ≥ 7% (n=161); the placebo group had a mean change in weight of -0.8 kg and 6.0% of subjects had an increase in body weight of ≥ 7% (n=168).

5.7 Orthostatic Hypotension and Syncope

Paliperidone can induce orthostatic hypotension and syncope in some patients because of its alpha- adrenergic blocking activity. Syncope was reported in < 1% (4/1293) of subjects treated with another once-a-month paliperidone palmitate extended-release injectable suspension (PP1M) in the recommended maintenance dose range of 39 mg to 234 mg in the four fixed- dose, double-blind, placebo-controlled trials compared with 0% (0/510) of subjects treated with placebo. In the four fixed-dose efficacy studies in subjects with schizophrenia, orthostatic hypotension was reported as an adverse event by < 1% (2/1293) of the PP1M-treated subjects compared to 0% (0/510) with placebo. Incidences of orthostatic hypotension and syncope in the long-term studies in subjects with schizophrenia and schizoaffective disorder were similar to those observed in the short-term studies.

Use ERZOFRI with caution in patients with known cardiovascular disease (e.g., heart failure, history of myocardial infarction or ischemia, conduction abnormalities), cerebrovascular disease, or conditions that predispose the patient to hypotension (e.g., dehydration, hypovolemia, and treatment with antihypertensive medications). Monitoring of orthostatic vital signs should be considered in patients who are vulnerable to hypotension.

5.8 Falls

Somnolence, postural hypotension, motor and sensory instability have been reported with the use of antipsychotics, including paliperidone palmitate, which may lead to falls and, consequently, fractures or other fall-related injuries. For patients, particularly the elderly, with diseases, conditions, or medications that could exacerbate these effects, assess the risk of falls when initiating antipsychotic treatment and recurrently for patients on long-term antipsychotic therapy.

5.9 Leukopenia, Neutropenia, and Agranulocytosis

In clinical trial and/or postmarketing experience, events of leukopenia and neutropenia have been reported temporally related to antipsychotic agents, including once-a-month paliperidone palmitate extended-release injectable suspension (PP1M). Agranulocytosis has also been reported.

Possible risk factors for leukopenia/neutropenia include pre-existing low white blood cell count (WBC)/absolute neutrophil count (ANC) and history of drug-induced leukopenia/neutropenia. In patients with a history of a clinically significant low WBC/ANC or a drug-induced leukopenia/neutropenia, perform a complete blood count (CBC) frequently during the first few months of therapy. In such patients, consider discontinuation of ERZOFRI at the first sign of a clinically significant decline in WBC in the absence of other causative factors.

Monitor patients with clinically significant neutropenia for fever or other symptoms or signs of infection and treat promptly if such symptoms or signs occur. Discontinue ERZOFRI in patients with severe neutropenia (absolute neutrophil count < 1000/mm^3) and follow their WBC until recovery.

5.10 Hyperprolactinemia

Like other drugs that antagonize dopamine D2 receptors, paliperidone elevates prolactin levels and the elevation persists during chronic administration. Paliperidone has a prolactin-elevating effect similar to that seen with risperidone, a drug that is associated with higher levels of prolactin than other antipsychotic drugs.

Hyperprolactinemia, regardless of etiology, may suppress hypothalamic GnRH, resulting in reduced pituitary gonadotrophin secretion. This, in turn, may inhibit reproductive function by impairing gonadal steroidogenesis in both female and male patients. Galactorrhea, amenorrhea, gynecomastia, and impotence have been reported in patients receiving prolactin-elevating compounds. Long-standing hyperprolactinemia when associated with hypogonadism may lead to decreased bone density in both female and male subjects.

Tissue culture experiments indicate that approximately one-third of human breast cancers are prolactin dependent in vitro, a factor of potential importance if the prescription of these drugs is considered in a patient with previously detected breast cancer. An increase in the incidence of pituitary gland, mammary gland, and pancreatic islet cell neoplasia (mammary adenocarcinomas, pituitary and pancreatic adenomas) was observed in the risperidone carcinogenicity studies conducted in mice and rats [see Nonclinical Toxicology (13.1)]. Published epidemiologic studies have shown inconsistent results when exploring the potential association between hyperprolactinemia and breast cancer.

Prolactin data from two long-term, double-blind, placebo-controlled studies with another PP1M are presented below; one study was in a population of patients with schizophrenia; the second study was in patients with schizoaffective disorder.

Schizophrenia

In a long-term maintenance trial of another once-a-month paliperidone palmitate extended-release injectable suspension (PP1M) in schizophrenia patients (Study 5) [see Clinical Studies (14.1)], elevations of prolactin to above the reference range (> 18 ng/mL in males and > 30 ng/mL in females) relative to open-label baseline at any time during the double- blind phase were noted in a higher percentage of the patients in the PP1M group than those in the placebo group in males (51.9% versus 29.0%) and in females (50.5% versus 42.9%). During the double-blind phase, 4 females (4.2%) in the PP1M group experienced potentially prolactin-related adverse reactions (amenorrhea N=2; galactorrhea N=1; menstruation irregular N=1), while 2 females (2.2%) in the placebo group experienced potentially prolactin-related adverse reactions (amenorrhea N=1; breast pain N=1). One male (0.9%) in the PP1M group experienced erectile dysfunction and 1 male (0.9%) in placebo group experienced gynecomastia.

Prior to the double-blind phase (during the 33-week open-label phase of the long-term maintenance trial), the mean (SD) serum prolactin values at baseline were 14.9 (22.3) ng/mL in males (N=490) and 35.2 (39.6) ng/mL in females (N=358). At the end of the open-label phase, mean (SD) prolactin values were 24.7 (22.5) ng/mL in males (N=470) and 59.5 (38.1) ng/mL in females (N=333). During the open-label phases 49.2% of females and 47.7% of males experienced elevations of prolactin above the reference range relative to baseline, and a higher proportion of females experienced potentially prolactin-related adverse reactions compared to males (5.3% versus 1.8%). Amenorrhea (2.5%) in females and no single potentially prolactin-related adverse reaction in males were observed with a rate greater than 2%.

Schizoaffective Disorder

In a long-term maintenance trial of another PP1M in patients with schizoaffective disorder (Study SCA-3004) see Clinical Studies (14.2), elevations of prolactin to above the reference range (> 13.13 ng/mL in males and > 26.72 ng/mL in females) relative to open-label baseline at any time during the 15-month double-blind phase were noted in a higher percentage of patients in the PP1M group than those in the placebo group in males (55.6% versus 23.2%) and in females (44.3% versus 25.0%). During the 15-month double-blind phase, 11 females (13.9%) in the PP1M group had 14 potentially prolactin-related adverse reactions (hyperprolactinemia N=3; blood prolactin increased N=4; libido decreased N=1; amenorrhea N=3; galactorrhea N=3), while 5 females (5.8%) in the placebo group had 6 potentially prolactin-related adverse reactions (hyperprolactinemia N=2; blood prolactin increased N=1; amenorrhea N=2; galactorrhea N=1). Six males (7.1%) in the PP1M group experienced 6 potentially prolactin-related adverse reactions (hyperprolactinemia N=4; libido decreased N=1; erectile dysfunction N=1), while 1 male (1.2%) in the placebo group experienced adverse reaction of blood prolactin increased.

Prior to the 15-month double-blind phase (during the 25-week open-label phase of the long-term maintenance trial), the mean (SD) serum prolactin values at baseline were 14.6 (14.0) ng/mL in males (N=352) and 39.1 (44.6) ng/mL in females (N=302). At the end of the open-label phase, mean (SD) prolactin values were 32.8 (17.2) ng/mL in males (N=275) and 72.4 (46.5) ng/mL in females (N=239). During the open-label phase, 48.9% of females and 53.3% of males experienced elevations of prolactin above the reference range relative to baseline, and a higher proportion of females experienced potentially prolactin-related adverse reactions compared to males (10.0% versus 9.0%). Amenorrhea (5.8%) and galactorrhea (2.9%) in females and libido decrease (2.8%) and erectile dysfunction (2.5%) in males were observed with a rate greater than 2%.

5.11 Potential for Cognitive and Motor Impairment

Somnolence, sedation, and dizziness were reported as adverse reactions in subjects treated with another once-a-month paliperidone palmitate extended-release injectable suspension (PP1M) [see Adverse Reactions (6.1)]. Antipsychotics, including ERZOFRI, have the potential to impair judgment, thinking, or motor skills. Patients should be cautioned about performing activities requiring mental alertness, such as operating hazardous machinery or operating a motor vehicle, until they are reasonably certain that paliperidone therapy does not adversely affect them.

5.12 Seizures

In the four fixed-dose double-blind placebo-controlled studies in subjects with schizophrenia, <1% (1 out of 1,293) of subjects treated with another once-a-month paliperidone palmitate extended-release injectable suspension (PP1M) in the recommended dose range of 39 mg to 234 mg experienced a convulsion compared with <1% (1 out of 510) of placebo-treated subjects who experienced a grand mal convulsion.

Like other antipsychotic drugs, ERZOFRI should be used cautiously in patients with a history of seizures or other conditions that potentially lower the seizure threshold. Conditions that lower the seizure threshold may be more prevalent in patients 65 years or older.

5.13 Dysphagia

Esophageal dysmotility and aspiration have been associated with antipsychotic drug use. ERZOFRI and other antipsychotic drugs should be used cautiously in patients at risk for aspiration.

5.14 Priapism

Drugs with alpha-adrenergic blocking effects have been reported to induce priapism. Although no cases of priapism have been reported in clinical trials with another once-a-month paliperidone palmitate extended-release injectable suspension (PP1M), priapism has been reported with oral paliperidone during postmarketing surveillance. Severe priapism may require surgical intervention.

5.15 Disruption of Body Temperature Regulation

Disruption of the body's ability to reduce core body temperature has been attributed to antipsychotic agents. Appropriate care is advised when prescribing ERZOFRI to patients who will be experiencing conditions which may contribute to an elevation in core body temperature, e.g., exercising strenuously, exposure to extreme heat, receiving concomitant medication with anticholinergic activity, or being subject to dehydration.

6 ADVERSE REACTIONS

The following are discussed in more detail in other sections of the labeling:

- Increased mortality in elderly patients with dementia-related psychosis [see Boxed Warning and Warnings and Precautions (5.1)]
- Cerebrovascular adverse reactions, including stroke, in elderly patients with dementia-related psychosis [see Warnings and Precautions (5.2)]
- Neuroleptic malignant syndrome [see Warnings and Precautions (5.3)]
- QT prolongation [see Warnings and Precautions (5.4)]
- Tardive dyskinesia [see Warnings and Precautions (5.5)]
- Metabolic changes [see Warnings and Precautions (5.6)]
- Orthostatic hypotension and syncope [see Warnings and Precautions (5.7)]
- Falls [see Warnings and Precautions (5.8)]
- Leukopenia, neutropenia, and agranulocytosis [see Warnings and Precautions (5.9)]
- Hyperprolactinemia [see Warnings and Precautions (5.10)]
- Potential for cognitive and motor impairment [see Warnings and Precautions (5.11)]
- Seizures [see Warnings and Precautions (5.12)]
- Dysphagia [see Warnings and Precautions (5.13)]
- Priapism [see Warnings and Precautions (5.14)]
- Disruption of body temperature regulation [see Warnings and Precautions (5.15)]

6.1 Clinical Trials Experience

Because clinical trials are conducted under widely varying conditions, adverse reaction rates observed in the clinical trials of a drug cannot be directly compared to rates in the clinical trials of another drug and may not reflect the rates observed in clinical practice.

The safety of ERZOFRI for the treatment of schizophrenia in adults and schizoaffective disorder in adults as monotherapy and as an adjunct to mood stabilizers or antidepressants is based upon adequate and well-controlled studies of another once-a-month paliperidone palmitate extended-release injectable suspension (also referred to as "PP1M" in this section). Below is a display of adverse reactions with another PP1M from those adequate and well-controlled studies.

Injection site reactions for ERZOFRI presented in this section (see "Pain and Injection Site Reactions with ERZOFRI" below) are based on pharmacokinetic studies.

Patient Exposure

The data described in this section are derived from a clinical trial database consisting of a total of 3,817 subjects (approximately 1,705 patient-years exposure) with schizophrenia who received at least one dose of PP1M in the recommended dose range of 39 mg to 234 mg and a total of 510 subjects with schizophrenia who received placebo. Among the 3,817 PP1M-treated subjects, 1,293 received PP1M in four fixed-dose, double- blind, placebo-controlled trials (one 9-week and three 13-week studies), 849 received PP1M in the maintenance trial (median exposure 229 days during the initial 33-week open-label phase of this study, of whom 205 continued to receive PP1M during the double-blind placebo-controlled phase of this study [median exposure 171 days]), and 1,675 received PP1M in five non-placebo controlled trials (three noninferiority active- comparator trials, one long-term open-label pharmacokinetic and safety study, and an injection site [deltoid-gluteal] cross-over trial). One of the 13-week studies included a 234 mg PP1M initiation dose followed by treatment with either 39 mg, 156 mg, or 234 mg every 4 weeks.

The safety of PP1M was also evaluated in a 15-month, long-term study comparing the other PP1M to selected oral antipsychotic therapies in adult subjects with schizophrenia. A total of 226 subjects received PP1M during the 15-month, open-label period of this study; 218 subjects received selected oral antipsychotic therapies. The safety of PP1M was similar to that seen in previous double-blind, placebo-controlled clinical trials in adult subjects with schizophrenia.

The safety of PP1M was also evaluated in a long-term study in adult subjects with schizoaffective disorder. A total of 667 subjects PP1M during the initial 25-week open-label period of this study (median exposure 147 days); 164 subjects continued to receive PP1M during the 15-month double-blind placebo-controlled period of this study (median exposure 446 days). Adverse reactions that occurred more frequently in the PP1M group than the placebo group (a 2% difference or more between groups) were weight increased, nasopharyngitis, headache, hyperprolactinemia, and pyrexia.

Adverse Reactions in Double-Blind, Placebo-Controlled Clinical Trials

Commonly Observed Adverse Reactions: The most common (at least 5% in any PP1M group) and likely drug-related (adverse events for which the drug rate is at least twice the placebo rate) adverse reactions from the double-blind, placebo-controlled trials in subjects with schizophrenia were injection site reactions, somnolence/sedation, dizziness, akathisia, and extrapyramidal disorder. No occurrences of adverse events reached this threshold in the long-term double-blind, placebo-controlled study in subjects with schizoaffective disorder.

Discontinuation of Treatment Due to Adverse Events: The percentage of subjects who discontinued due to adverse events in the four fixed-dose, double-blind, placebo-controlled schizophrenia trials were similar for PP1M- and placebo-treated subjects.

The percentage of subjects who discontinued due to adverse events in the open-label period of the long-term study in subjects with schizoaffective disorder was 7.5%. During the double-blind, placebo-controlled period of that study, the percentages of subjects who discontinued due to adverse events were 5.5% and 1.8% in PP1M- and placebo-treated subjects, respectively.

Dose-Related Adverse Reactions: Based on the pooled data from the four fixed-dose, double- blind, placebo-controlled trials in subjects with schizophrenia, among the adverse reactions that occurred with ≥ 2% incidence in the subjects treated with PP1M, only akathisia increased with dose. Hyperprolactinemia also exhibited a dose relationship, but did not occur at ≥ 2% incidence in PP1M-treated subjects from the four fixed-dose studies.

Adverse Reactions Occurring at an Incidence of 2% or More in a once-a-month paliperidone palmitate extended-release injectable suspension-Treated Patients: Table 9 lists the adverse reactions reported in 2% or more of PP1M -treated subjects and at a greater proportion than in the placebo group with schizophrenia in the four fixed-dose, double-blind, placebo-controlled trials.

Table 9: Incidences of Adverse Reactions 2% or More of a Once-a-Month Paliperidone Palmitate Extended-Release Injectable Suspension-Treated Patients (and Greater than Placebo) with Schizophrenia in Four Fixed-Dose, Double-Blind, Placebo-Controlled Trials
 |  | Once-a-Month Paliperidone Palmitate Extended-Release Injectable Suspension
System Organ Class Adverse Reactions | Placebo [Placebo group is pooled from all studies and included either deltoid or gluteal injection depending on study design.] (N=510) | 39 mg (N=130) | 78 mg (N=302) | 156 mg (N=312) | 234/39 mg [Initial deltoid injection of 234 mg followed by either 39 mg, 156 mg, or 234 mg every 4 weeks by deltoid or gluteal injection. Other dose groups (39 mg, 78 mg, and 156 mg) are from studies involving only gluteal injection. [see Clinical Studies (14.1)]] (N=160) | 234/156 mg (N=165) | 234/234 mg (N=163)
Total percentage of subjects with adverse reactions | 70 | 75 | 68 | 69 | 63 | 60 | 63
Gastrointestinal disorders
Abdominal discomfort/abdominal pain upper | 2 | 2 | 4 | 4 | 1 | 2 | 4
Diarrhea | 2 | 0 | 3 | 2 | 1 | 2 | 2
Dry mouth | 1 | 3 | 1 | 0 | 1 | 1 | 1
Nausea | 3 | 4 | 4 | 3 | 2 | 2 | 2
Toothache | 1 | 1 | 1 | 3 | 1 | 2 | 3
Vomiting | 4 | 5 | 4 | 2 | 3 | 2 | 2
General disorders and administration site conditions
Asthenia | 0 | 2 | 1 | <1 | 0 | 1 | 1
Fatigue | 1 | 1 | 2 | 2 | 1 | 2 | 1
Injection site reactions | 2 | 0 | 4 | 6 | 9 | 7 | 10
Infections and infestations
Nasopharyngitis | 2 | 0 | 2 | 2 | 4 | 2 | 2
Upper respiratory tract infection | 2 | 2 | 2 | 2 | 1 | 2 | 4
Urinary tract infection | 1 | 0 | 1 | <1 | 1 | 1 | 2
Investigations
Weight increased | 1 | 4 | 4 | 1 | 1 | 1 | 2
Musculoskeletal and connective tissue disorders
Back pain | 2 | 2 | 1 | 3 | 1 | 1 | 1
Musculoskeletal stiffness | 1 | 1 | <1 | <1 | 1 | 1 | 2
Myalgia | 1 | 2 | 1 | <1 | 1 | 0 | 2
Pain in extremity | 1 | 0 | 2 | 2 | 2 | 3 | 0
Nervous system disorders
Akathisia | 3 | 2 | 2 | 3 | 1 | 5 | 6
Dizziness | 1 | 6 | 2 | 4 | 1 | 4 | 2
Extrapyramidal disorder | 1 | 5 | 2 | 3 | 1 | 0 | 0
Headache | 12 | 11 | 11 | 15 | 11 | 7 | 6
Somnolence/sedation | 3 | 5 | 7 | 4 | 1 | 5 | 5
Psychiatric disorders
Agitation | 7 | 10 | 5 | 9 | 8 | 5 | 4
Anxiety | 7 | 8 | 5 | 3 | 5 | 6 | 6
Nightmare | <1 | 2 | 0 | 0 | 0 | 0 | 0
Respiratory, thoracic and mediastinal disorders
Cough | 1 | 2 | 3 | 1 | 0 | 1 | 1
Vascular disorders
Hypertension | 1 | 2 | 1 | 1 | 1 | 1 | 0
Percentages are rounded to whole numbers. Table includes adverse reactions that were reported in 2% or more of subjects in any of the once-a-month paliperidone palmitate extended-release injectable suspension dose groups and which occurred at greater incidence than in the placebo group.

Adverse reactions for which the once-a-month paliperidone palmitate extended-release injectable suspension incidence was equal to or less than placebo are not listed in the table, but included the following: dyspepsia, psychotic disorder, schizophrenia, and tremor. The following terms were combined: somnolence/sedation, breast tenderness/breast pain, abdominal discomfort/abdominal pain upper/stomach discomfort, and tachycardia/sinus tachycardia/heart rate increased. All injection site reaction-related adverse reactions were collapsed and are grouped under "Injection site reactions".

Other Adverse Reactions Observed During the Clinical Trial Evaluation of Once-a-Month Paliperidone Palmitate Extended-Release Injectable Suspension

The following list does not include reactions: 1) already listed in previous tables or elsewhere in labeling, 2) for which a drug cause was remote, 3) which were so general as to be uninformative, or 4) which were not considered to have significant clinical implications.

Cardiac disorders: atrioventricular block first degree, bradycardia, bundle branch block, palpitations, postural orthostatic tachycardia syndrome, tachycardia

Ear and labyrinth disorders: vertigo

Eye disorders: eye movement disorder, eye rolling, oculogyric crisis, vision blurred

Gastrointestinal disorders: constipation, dyspepsia, flatulence, salivary hypersecretion

Immune system disorders: hypersensitivity

Investigations: alanine aminotransferase increased, aspartate aminotransferase increased, electrocardiogram abnormal

Metabolism and nutrition disorders: decreased appetite, hyperinsulinemia, increased appetite

Musculoskeletal and connective tissue disorders: arthralgia, joint stiffness, muscle rigidity, muscle spasms, muscle tightness, muscle twitching, nuchal rigidity

Nervous system disorders: bradykinesia, cerebrovascular accident, cogwheel rigidity, convulsion, dizziness postural, drooling, dysarthria, dyskinesia, dystonia, hypertonia, lethargy, oromandibular dystonia, parkinsonism, psychomotor hyperactivity, syncope

Psychiatric disorders: insomnia, libido decreased, restlessness

Reproductive system and breast disorders: amenorrhea, breast discharge, breast enlargement/breast swelling, breast tenderness/breast pain, ejaculation disorder, erectile dysfunction, galactorrhea, gynecomastia, menstrual disorder, menstruation delayed, menstruation irregular, sexual dysfunction

Respiratory, thoracic and mediastinal disorders: nasal congestion

Skin and subcutaneous tissue disorders: drug eruption, pruritus, pruritus generalized, rash, urticaria

Demographic Differences

An examination of population subgroups in the double-blind placebo-controlled trials did not reveal any evidence of differences in safety on the basis of age, gender, or race alone; however, there were few subjects 65 years of age and older.

Extrapyramidal Symptoms (EPS)

Pooled data from the two double-blind, placebo-controlled, 13-week, fixed-dose trials in adult subjects with schizophrenia provided information regarding EPS. Several methods were used to measure EPS: (1) the Simpson-Angus global score which broadly evaluates parkinsonism, (2) the Barnes Akathisia Rating Scale global clinical rating score which evaluates akathisia, (3) the Abnormal Involuntary Movement Scale scores which evaluates dyskinesia, and (4) use of anticholinergic medications to treat EPS (Table 10), and (5) incidence of spontaneous reports of EPS (Table 11).

Table 10: Extrapyramidal Symptoms (EPS) Assessed by Incidence of Rating Scales and Use of Anticholinergic Medication – Schizophrenia Studies in Adults
 | Percentage of Subjects
 |  | Once-a-Month Paliperidone Palmitate Extended-Release Injectable Suspension
Scale | Placebo (N=262) | 39 mg (N=130) | 78 mg (N=223) | 156 mg (N=228)
Parkinsonism [For parkinsonism, percent of subjects with Simpson-Angus Total score > 0.3 at endpoint (Total score defined as total sum of items score divided by the number of items)] | 9 | 12 | 10 | 6
Akathisia [For Akathisia, percent of subjects with Barnes Akathisia Rating Scale global score ≥ 2 at endpoint] | 5 | 5 | 6 | 5
Dyskinesia [For Dyskinesia, percent of subjects with a score ≥ 3 on any of the first 7 items or a score ≥ 2 on two or more of any of the first 7 items of the Abnormal Involuntary Movement Scale at endpoint] | 3 | 4 | 6 | 4
Use of Anticholinergic Medications [Percent of subjects who received anticholinergic medications to treat EPS] | 12 | 10 | 12 | 11

Table 11: Extrapyramidal Symptoms (EPS)-Related Events by MedDRA Preferred Term – Schizophrenia Studies in Adults
 | Percentage of Subjects
 |  | Once-a-Month Paliperidone Palmitate Extended-Release Injectable Suspension
EPS Group | Placebo (N=262) | 39 mg (N=130) | 78 mg (N=223) | 156 mg (N=228)
Overall percentage of subjects with EPS-related adverse events | 10 | 12 | 11 | 11
Parkinsonism | 5 | 6 | 6 | 4
Hyperkinesia | 2 | 2 | 2 | 4
Tremor | 3 | 2 | 2 | 3
Dyskinesia | 1 | 2 | 3 | 1
Dystonia | 0 | 1 | 1 | 2
Parkinsonism group includes: Extrapyramidal disorder, hypertonia, musculoskeletal stiffness, parkinsonism, drooling, masked facies, muscle tightness, hypokinesia
Hyperkinesia group includes: Akathisia, restless legs syndrome, restlessness
Dyskinesia group includes: Dyskinesia, choreoathetosis, muscle twitching, myoclonus, tardive dyskinesia
Dystonia group includes: Dystonia, muscle spasms

The results across all phases of the maintenance trial in subjects with schizophrenia exhibited comparable findings. In the 9-week, fixed-dose, double-blind, placebo-controlled trial, the proportions of parkinsonism and akathisia assessed by incidence of rating scales were higher in the PP1M 156 mg group (18% and 11%, respectively) than in the PP1M 78 mg group (9% and 5%, respectively) and placebo group (7% and 4%, respectively).

In the 13-week study in subjects with schizophrenia involving 234 mg initiation dosing, the incidence of any EPS was similar to that of the placebo group (8%), but exhibited a dose-related pattern with 6%, 10%, and 11% in the PP1M 234/39 mg, 234/156 mg, and 234/234 mg groups, respectively. Hyperkinesia was the most frequent category of EPS-related adverse events in this study, and was reported at a similar rate between the placebo (4.9%) and PP1M 234/156 mg (4.8%) and 234/234 mg (5.5%) groups, but at a lower rate in the 234/39 mg group (1.3%).

In the long-term study in subjects with schizoaffective disorder, EPS reported during the 25-week open-label PP1M treatment included hyperkinesia (12.3%), parkinsonism (8.7%), tremor (3.4%), dyskinesia (2.5%), and dystonia (2.1%). During the 15-month double-blind treatment, the incidence of any EPS was similar to that of the placebo group (8.5% and 7.1% respectively). The most commonly reported treatment-emergent EPS-related adverse events (> 2%) in any treatment group in the double-blind phase of the study (PP1M versus placebo) were hyperkinesia (3.7% versus 2.9%), parkinsonism (3.0% versus 1.8%), and tremor (1.2% versus 2.4%).

Dystonia

Symptoms of dystonia, prolonged abnormal contractions of muscle groups, may occur in susceptible individuals during the first few days of treatment. Dystonic symptoms include: spasm of the neck muscles, sometimes progressing to tightness of the throat, swallowing difficulty, difficulty breathing, and/or protrusion of the tongue. While these symptoms can occur at low doses, they occur more frequently and with greater severity with high potency and at higher doses of first-generation antipsychotic drugs. An elevated risk of acute dystonia is observed in males and younger age groups.

Pain Assessment and Injection Site Reactions

In the pooled data from the two 13-week, fixed-dose, double-blind, placebo-controlled trials of another PP1M in subjects with schizophrenia, the mean intensity of injection pain reported by subjects using a visual analog scale (0 = no pain to 100 = unbearably painful) decreased in all treatment groups from the first to the last injection (placebo: 10.9 to 9.8; 39 mg: 10.3 to 7.7; 78 mg: 10.0 to 9.2; 156 mg: 11.1 to 8.8). The results from both the 9-week, fixed-dose, double-blind, placebo-controlled trial and the double-blind phase of the maintenance trial exhibited comparable findings.

In the 13-week study involving 234 mg initiation dosing in subjects with schizophrenia, occurrences of induration, redness, or swelling, as assessed by blinded study personnel, were infrequent, generally mild, decreased over time, and similar in incidence between the PP1M and placebo groups. Investigator ratings of injection pain were similar for the placebo and PP1M groups. Investigator evaluations of the injection site after the first injection for redness, swelling, induration, and pain were rated as absent for 69-100% of subjects in both the PP1M and placebo groups. At Day 92, investigators rated absence of redness, swelling, induration, and pain in 95-100% of subjects in both the PP1M and placebo groups.

ERZOFRI was evaluated in 281 patients with schizophrenia or schizoaffective disorder in an open-label randomized parallel arm study. The percentage of patients in the open-label study reporting injection site-related adverse reactions at the first injection for patients treated with ERZOFRI (all reported as injection site pain) was similar to the percentage of patients treated with another PP1M.

Additional Adverse Reactions Reported in Clinical Trials with Oral Paliperidone

The following is a list of additional adverse reactions that have been reported in clinical trials with oral paliperidone:

Cardiac disorders: bundle branch block left, sinus arrhythmia

Gastrointestinal disorders: abdominal pain, small intestinal obstruction

General disorders and administration site conditions: edema, edema peripheral

Immune system disorders: anaphylactic reaction

Infections and infestations: rhinitis

Musculoskeletal and connective tissue disorders: musculoskeletal pain, torticollis, trismus

Nervous system disorders: grand mal convulsion, parkinsonian gait, transient ischemic attack

Psychiatric disorders: sleep disorder

Reproductive system and breast disorders: breast engorgement

Respiratory, thoracic and mediastinal disorders: pharyngolaryngeal pain, pneumonia aspiration

Skin and subcutaneous tissue disorders: rash papular

Vascular disorders: hypotension, ischemia

6.2 Postmarketing Experience

The following adverse reactions have been identified during post-approval use of paliperidone; because these reactions were reported voluntarily from a population of uncertain size, it is not always possible to reliably estimate their frequency or establish a causal relationship to drug exposure: angioedema, catatonia, ileus, somnambulism, swollen tongue, thrombotic thrombocytopenic purpura, urinary incontinence, and urinary retention.

Cases of anaphylactic reaction after injection with another once-a-month paliperidone palmitate extended-release injectable suspension product have been reported during postmarketing experience in patients who have previously tolerated oral risperidone or oral paliperidone.

Paliperidone is the major active metabolite of risperidone. Adverse reactions reported with oral risperidone and risperidone long-acting injection can be found in the Adverse Reactions (6) sections of the package inserts for those products.

7 DRUG INTERACTIONS

7.1 Drugs Having Clinically Important Interactions with ERZOFRI

Because paliperidone palmitate is hydrolyzed to paliperidone [see Clinical Pharmacology (12.3)], results from studies with oral paliperidone should be taken into consideration when assessing drug-drug interaction potential.

Table 12 presents clinically significant drug interactions with ERZOFRI.

Table 12: Clinically Important Drug Interactions with ERZOFRI
Centrally Acting Drugs and Alcohol
Clinical Rationale: | Given the primary CNS effects of paliperidone, concomitant use of centrally acting drugs and alcohol may modulate the CNS effects of ERZOFRI.
Clinical Recommendation: | ERZOFRI should be used with caution in combination with other centrally acting drugs and alcohol [see Adverse Reactions (6.1, 6.2)].
Drugs with Potential for Inducing Orthostatic Hypotension
Clinical Rationale: | Because ERZOFRI has the potential for inducing orthostatic hypotension, an additive effect may occur when ERZOFRI is administered with other therapeutic agents that have this potential [see Warnings and Precautions (5.7)].
Clinical Recommendation: | Monitor orthostatic vital signs in patients who are vulnerable to hypotension [see Warnings and Precautions (5.7)].
Strong Inducers of CYP3A4 and P-gp
Clinical Rationale: | The concomitant use of paliperidone and strong inducers of CYP3A4 and P-gp may decrease the exposure of paliperidone [see Clinical Pharmacology (12.3)].
Clinical Recommendation: | Avoid using CYP3A4 and/or P-gp inducers with ERZOFRI during the 1-month dosing interval, if possible. If administering a strong inducer is necessary, consider managing the patient using paliperidone extended-release tablets [see Dosage and Administration (2.5)].
Levodopa and Other Dopamine Agonists
Clinical Rationale: | Paliperidone may antagonize the effect of levodopa and other dopamine agonists.
Clinical Recommendation: | Monitor and manage patient as clinically appropriate.

7.2 Drugs Having No Clinically Important Interactions with ERZOFRI

Based on pharmacokinetic studies with oral paliperidone, no dosage adjustment of ERZOFRI is required when administered with valproate [see Clinical Pharmacology (12.3)]. Additionally, no dosage adjustment is necessary for valproate when co-administered with ERZOFRI [See Clinical Pharmacology (12.3)].

Pharmacokinetic interaction between lithium and ERZOFRI is also unlikely.

Paliperidone is not expected to cause clinically important pharmacokinetic interactions with drugs that are metabolized by cytochrome P450 isozymes. In vitro studies indicate that CYP2D6 and CYP3A4 may be involved in paliperidone metabolism; however, there is no evidence in vivo that inhibitors of these enzymes significantly affect the metabolism of paliperidone. Paliperidone is not a substrate of CYP1A2, CYP2A6, CYP2C9, and CYP2C19; an interaction with inhibitors or inducers of these isozymes is unlikely. [see Clinical Pharmacology (12.3)]

8 USE IN SPECIFIC POPULATIONS

8.1 Pregnancy

Pregnancy Exposure Registry

There is a pregnancy exposure registry that monitors pregnancy outcomes in women exposed to atypical antipsychotics, including ERZOFRI, during pregnancy. Healthcare providers are encouraged to advise patients to register by contacting the National Pregnancy Registry for Atypical Antipsychotics at 1-866-961-2388 or online at http://womensmentalhealth.org/clinical- and-research-programs/pregnancyregistry/.

Risk Summary

Neonates exposed to antipsychotic drugs during the third trimester of pregnancy are at risk for extrapyramidal and/or withdrawal symptoms following delivery (see Clinical Considerations). Overall, available data from published epidemiologic studies of pregnant women exposed to paliperidone have not established a drug-associated risk for major birth defects, miscarriage, or adverse maternal or fetal outcomes (see Data). There are risks to the mother associated with untreated schizophrenia and with exposure to antipsychotics, including ERZOFRI, during pregnancy (see Clinical Considerations). Paliperidone has been detected in plasma in adult subjects up to 176 days after a single-dose administration of ERZOFRI [see Clinical Pharmacology (12.3)], and the clinical significance of ERZOFRI administered before pregnancy or anytime during pregnancy is not known.

The estimated background risk of major birth defects and miscarriage for the indicated population is unknown. All pregnancies have a background risk of birth defects, loss, or other adverse outcomes. In the U.S. general population, the estimated background risk of major birth defects and miscarriage in clinically recognized pregnancies is 2% to 4% and 15% to 20%, respectively.

In animal reproduction studies, there were no treatment related effects on the offspring when pregnant rats were injected intramuscularly with paliperidone palmitate during the period of organogenesis at doses up to 10 times the maximum recommended human dose (MRHD) of 234 mg paliperidone palmitate based on mg/m^2 body surface area (BSA). There were no increases in fetal abnormalities when pregnant rats and rabbits were treated orally with paliperidone during the period of organogenesis with up to 8 times the MRHD of 12 mg of paliperidone based on mg/m^2 BSA. Additional reproduction toxicity studies were conducted with orally administered risperidone, which is extensively converted to paliperidone (see Animal data).

Clinical Considerations

Disease-associated maternal and/or embryo/fetal risk

There is a risk to the mother from untreated schizophrenia, including increased risk of relapse, hospitalization, and suicide. Schizophrenia and bipolar I disorder are associated with increased adverse perinatal outcomes, including preterm birth. It is not known if this is a direct result of the illness or other comorbid factors.

Fetal/Neonatal Adverse Reactions

Extrapyramidal and/or withdrawal symptoms, including agitation, hypertonia, hypotonia, tremor, somnolence, respiratory distress, and feeding disorder have been reported in neonates who were exposed to antipsychotic drugs, including paliperidone palmitate, during the third trimester of pregnancy. These symptoms have varied in severity. Monitor neonates exhibiting extrapyramidal and/or withdrawal symptoms and manage symptoms appropriately. Some neonates recovered within hours or days without specific treatment; others required prolonged hospitalization.

Data

Human Data

Published data from observational studies, birth registries, and case reports on the use of atypical antipsychotics during pregnancy do not report a clear association with antipsychotics and major birth defects. A prospective observational study including 6 women treated with risperidone, the parent compound of paliperidone, demonstrated placental passage of risperidone and paliperidone. A retrospective cohort study from a Medicaid database of 9,258 women exposed to antipsychotics during pregnancy did not indicate an overall increased risk for major birth defects. There was a small increase in the risk of major birth defects (RR= 1.26, 95% CI 1.02-1.56) and of cardiac malformations (RR=1.26, 95% CI 0.88-1.81) in a subgroup of 1,566 women exposed to the parent compound of paliperidone, risperidone, during the first trimester of pregnancy; however, there is no mechanism of action to explain the difference in malformation rates.

Animal Data

There were no treatment-related effects on the offspring when pregnant rats were injected intramuscularly with paliperidone palmitate extended-release injectable suspension during the period of organogenesis at doses up to 250 mg/kg, which is 10 times MRHD of 234 mg paliperidone palmitate as a monthly maintenance dose based on body surface area (BSA).

In animal reproduction studies, there were no increases in fetal abnormalities when pregnant rats and rabbits were treated orally with paliperidone during the period of organogenesis with up to 8 times the MRHD of 12 mg based on BSA.

Additional reproduction toxicity studies were conducted with orally administered risperidone, which is extensively converted to paliperidone. Cleft palate was observed in the offspring of pregnant mice treated with risperidone at 3 to 4 times the MRHD of 16 mg based on BSA; maternal toxicity occurred at 4 times the MHRD. There was no evidence of teratogenicity in embryo-fetal developmental toxicity studies with risperidone in rats and rabbits at doses up to 6 times the MRHD of 16 mg risperidone based on BSA. When the offspring of pregnant rats, treated with risperidone at 0.6 times the MRHD based on BSA, reached adulthood, learning was impaired. Increased neuronal cell death occurred in the fetal brains of the offspring of pregnant rats treated at 0.5 to 1.2 times the MRHD; the postnatal development and growth of the offspring were delayed.

In rat reproduction studies with risperidone, pup deaths occurred at oral doses which are less than the MRHD of risperidone based on BSA; it is not known whether these deaths were due to a direct effect on the fetuses or pups or, to effects on the dams (see RISPERDAL® prescribing information).

8.2 Lactation

Risk Summary

Limited data from published literature report the presence of paliperidone in human breast milk. There is no information on the effects on the breastfed infant or the effects on milk production; however, there are reports of sedation, failure to thrive, jitteriness, and extrapyramidal symptoms (tremors and abnormal muscle movements) in breastfed infants exposed to paliperidone's parent compound, risperidone (see Clinical Considerations). Paliperidone has been detected in plasma in adult subjects up to 176 days after a single-dose administration of ERZOFRI [see Clinical Pharmacology (12.3)], and the clinical significance on the breastfed infant is not known. The developmental and health benefits of breastfeeding should be considered along with the mother's clinical need for ERZOFRI and any potential adverse effects on the breastfed child from ERZOFRI or from the mother's underlying condition.

Clinical Considerations

Infants exposed to ERZOFRI through breastmilk should be monitored for excess sedation, failure to thrive, jitteriness, and extrapyramidal symptoms (tremors and abnormal muscle movements).

8.3 Females and Males of Reproductive Potential

Infertility

Females

Based on the pharmacologic action of paliperidone (D2 receptor antagonism), treatment with ERZOFRI may result in an increase in serum prolactin levels, which may lead to a reversible reduction in fertility in females of reproductive potential [see Warnings and Precautions (5.10)].

8.4 Pediatric Use

Safety and effectiveness of ERZOFRI in pediatric patients have not been established.

Juvenile Animal Toxicity Data

In a study in which juvenile rats were treated with oral paliperidone from Days 24 to 73 of age, a reversible impairment of performance in a test of learning and memory was seen, in females only, with a no-effect dose of 0.63 mg/kg/day, which produced plasma levels (AUC) of paliperidone similar to those in adolescents dosed at a 12 mg/day oral dose. No other consistent effects on neurobehavioral or reproductive development were seen up to the highest dose tested (2.5 mg/kg/day), which produced plasma levels of paliperidone 2-3 times those in adolescents.

Juvenile dogs were treated for 40 weeks with oral risperidone, which is extensively metabolized to paliperidone in animals and humans, at doses of 0.31, 1.25, or 5 mg/kg/day. Decreased bone length and density were seen with a no-effect dose of 0.31 mg/kg/day, which produced plasma levels (AUC) of risperidone plus paliperidone, which were similar to those in children and adolescents receiving the MRHD of oral risperidone. In addition, a delay in sexual maturation was seen at all doses in both males and females. The above effects showed little or no reversibility in females after a 12-week drug-free recovery period.

The long-term effects of ERZOFRI on growth and sexual maturation have not been fully evaluated in pediatric patients.

8.5 Geriatric Use

Clinical studies of ERZOFRI did not include sufficient numbers of subjects aged 65 and over to determine whether they respond differently from younger subjects. Other reported clinical experience has not identified differences in responses between the elderly and younger patients.

Paliperidone palmitate is substantially excreted by the kidney and clearance is decreased in patients with renal impairment [see Clinical Pharmacology (12.3)], who should be given reduced doses. Because geriatric patients are more likely to have decreased renal function, adjust dose based on renal function [see Dosage and Administration (2.4)].

8.6 Renal Impairment

Use of ERZOFRI is not recommended in patients with moderate or severe renal impairment (creatinine clearance < 50 mL/min). Dose reduction is recommended for patients with mild renal impairment (creatinine clearance ≥ 50 mL/min to < 80 mL/min) [see Dosage and Administration (2.4) and Clinical Pharmacology (12.3)].

8.7 Hepatic Impairment

ERZOFRI has not been studied in patients with hepatic impairment. Based on a study with oral paliperidone, no dose adjustment is required in patients with mild or moderate hepatic impairment. Paliperidone has not been studied in patients with severe hepatic impairment [see Clinical Pharmacology (12.3)].

8.8 Patients with Parkinson's Disease or Lewy Body Dementia

Patients with Parkinson's Disease or Dementia with Lewy Bodies can experience increased sensitivity to ERZOFRI. Manifestations can include confusion, obtundation, postural instability with frequent falls, extrapyramidal symptoms, and clinical features consistent with neuroleptic malignant syndrome.

10 OVERDOSAGE

Human Experience

While experience with paliperidone overdose is limited, among the few cases of overdose reported in premarketing trials with oral paliperidone, the highest estimated ingestion was 405 mg. Observed signs and symptoms included extrapyramidal symptoms and gait unsteadiness. Other potential signs and symptoms include those resulting from an exaggeration of paliperidone's known pharmacological effects, i.e., drowsiness and sedation, tachycardia and hypotension, and QT prolongation. Torsades de pointes and ventricular fibrillation have been reported in a patient in the setting of overdose with oral paliperidone.

Paliperidone is the major active metabolite of risperidone. Refer to the OVERDOSAGE section of the risperidone prescribing information for overdose experience with risperidone.

Management of Overdosage

There is no specific antidote to paliperidone. Provide supportive care, including close medical supervision and monitoring. Treatment should consist of general measures employed in the management of overdosage with any drug. Consider the possibility of multiple drug overdosage. Ensure an adequate airway, oxygenation, and ventilation. Monitor cardiac rhythm and vital signs. Use supportive and symptomatic measures.

Consider the pharmacokinetic profile of ERZOFRI and the half-life of paliperidone when assessing treatment needs and recovery.

Consider contacting the Poison Help Line (1-800-222-1222) or medical toxicologist for additional overdosage management recommendations.

11 DESCRIPTION

ERZOFRI (paliperidone palmitate) extended-release injectable suspension contains a racemic mixture of (+)- and (-)- paliperidone palmitate. Paliperidone palmitate, is an atypical antipsychotic belonging to the chemical class of benzisoxazole derivatives. The chemical name is (9RS)-3-[2-[4-(6-Fluoro-1,2-benzisoxazol-3-yl)piperidin-1-yl]ethyl]-2-methyl-4-oxo-6,7,8,9-tetrahydro-4H-pyrido[1,2-a]pyrimadin-9-yl hexadecanoate. Its molecular formula is C39H57FN4O4 and its molecular weight is 664.89. The structural formula is:

Paliperidone palmitate is very slightly soluble in ethanol and methanol, practically insoluble in water, and slightly soluble in ethyl acetate.

ERZOFRI is available as a white to off-white sterile aqueous extended-release suspension for intramuscular injection in the following dose strengths of paliperidone palmitate (deliverable volume) in single-dose prefilled syringes: 39 mg (0.25 mL), 78 mg (0.5 mL), 117 mg (0.75 mL), 156 mg (1 mL), 234 mg (1.5 mL), and 351 mg (2.25 mL). The drug product hydrolyzes in vivo to the active moiety, paliperidone, resulting in dose strengths of 25 mg, 50 mg, 75 mg, 100 mg, 150 mg, and 225 mg of paliperidone, respectively.

The inactive ingredients are citric acid monohydrate (5 mg/mL), dibasic sodium phosphate anhydrous (5 mg/mL), monobasic sodium phosphate monohydrate (2.5 mg/mL), polyethylene glycol 4000 (30 mg/mL), polysorbate 20 (12 mg/mL), sodium hydroxide to adjust pH, and water for injection. The drug product pH is 6.5 to 7.5.

12 CLINICAL PHARMACOLOGY

12.1 Mechanism of Action

Paliperidone palmitate is hydrolyzed to paliperidone [see Clinical Pharmacology (12.3)]. Paliperidone is the major active metabolite of risperidone. The mechanism of action of paliperidone in the listed indications is unclear. However, the drug's effect in schizophrenia could be mediated through a combination of central dopamine Type 2 (D2) and serotonin Type 2 (5HT2A) receptor antagonism.

12.2 Pharmacodynamics

Paliperidone is an antagonist at the central dopamine Type 2 (D2) and serotonin Type 2 (5HT2A) receptors with binding affinities (Ki values) of 1.6-2.8 nM for D2 and 0.8-1.2 nM for 5HT2A receptors. Paliperidone also acts as an antagonist at the α1 and α2 adrenergic receptors and H1 histaminergic receptors. Paliperidone has no affinity for cholinergic muscarinic or β1- and β2-adrenergic receptors. The pharmacological activity of the (+)- and (-)- paliperidone enantiomers is qualitatively and quantitatively similar.

12.3 Pharmacokinetics

The overall exposures (AUC) of paliperidone following another once-a-month paliperidone palmitate extended-release injectable suspension (also referred to as "PP1M" in this section) administration was dose-proportional over a dose range of 39 mg to 234 mg, and peak plasma concentrations (Cmax) were less than dose-proportional for doses exceeding 78 mg. Steady state plasma exposures of ERZOFRI are reached 7 days after the first injection.

Absorption

After intramuscular injection, paliperidone palmitate is hydrolyzed to paliperidone and absorbed into the systemic circulation. Following a single intramuscular dose of ERZOFRI, the plasma concentrations of paliperidone gradually rise to reach maximum plasma concentrations at a median Tmax of 16 to 28 days. The release of the drug starts as early as day 1 and lasts for as long as 176 days.

Following multiple intramuscular injections of ERZOFRI (351 mg on day 1 and 156 mg on day 29 and every 28 days for a total of 6 consecutive injections) in patients, the geometric least square mean Cmax, trough plasma concentrations (Ctrough) and average plasma concentrations (Cavg) were 43.7 ng/mL, 28.5 ng/mL and 30.3 ng/mL, respectively, during the initial regimen period; at steady state, Cmax-ss, Ctrough,ss and AUCtau-ss were 42.6 ng/mL, 28.3 ng/mL and 909 ng*hr/mL, respectively.

Following multiple intramuscular injections of another PP1M (234 mg on day 1 and 156 mg on day 8 and every 28 days for a total of 7 consecutive injections), the geometric least square mean Cmax, Ctrough and Cavg were 58.7 ng/mL, 30.1 ng/mL and 37.8 ng/mL, respectively, during the initial regimen period; at steady state, Cmax-ss, Ctrough,ss and AUCtau-ss of another once-a-month paliperidone palmitate extended-release injectable suspension for paliperidone were 43.8 ng/mL, 30.4 ng/mL and 953 ng*hr/mL, respectively.

Following intramuscular injection of a single dose of ERZOFRI 156 mg in the deltoid muscle, the geometric mean Cmax was approximately 43% higher compared with injections of 156 mg in the gluteal muscle. Following intramuscular injection of a single dose of ERZOFRI 351 mg in the deltoid muscle, the geometric mean Cmax was approximately 21% higher compared with injections of 351 mg in the gluteal muscle. Over the dose range of 39 mg to 234 mg, the AUCinf after a single dose injection in the deltoid muscle was comparable to the AUCinf after a single dose injection in the gluteal muscle.

Following intramuscular injection of single doses (39 mg to 234 mg) of another PP1M in the deltoid muscle, on average, a 28% higher Cmax was observed compared with injection in the gluteal muscle. The mean steady-state peak:trough ratio for PP1M dose of 156 mg was 1.8 following gluteal administration and 2.2 following deltoid administration.

Following administration of paliperidone palmitate, the (+) and (-) enantiomers of paliperidone interconvert, reaching an AUC (+) to (-) ratio of approximately 1.6 to 1.8.

Distribution

Based on a population analysis of data from ERZOFRI clinical trials, the apparent volume of distribution of paliperidone is 2840 L.

The plasma protein binding of racemic paliperidone is 74%.

Elimination

Metabolism

Four metabolic pathways have been identified in vivo, none of which accounted for more than 10% of the dose: dealkylation, hydroxylation, dehydrogenation, and benzisoxazole scission. Although in vitro studies suggested a role for CYP2D6 and CYP3A4 in the metabolism of paliperidone, there is no evidence in vivo that these isozymes play a significant role in the metabolism of paliperidone. Population pharmacokinetics analyses indicated no discernible difference on the apparent clearance of paliperidone after administration of oral paliperidone between extensive metabolizers and poor metabolizers of CYP2D6 substrates.

The median apparent half-life of paliperidone following ERZOFRI single-dose administration at 156 mg is approximately 27 days.

Excretion

In a study with oral immediate-release ^14C-paliperidone, one week following administration of a single oral dose of 1 mg immediate-release ^14C-paliperidone, 59% of the dose was excreted unchanged into urine, indicating that paliperidone is not extensively metabolized in the liver. Approximately 80% of the administered radioactivity was recovered in urine and 11% in the feces.

Drug Interaction Studies

No specific drug interaction studies have been performed with ERZOFRI. The information below is obtained from studies with oral paliperidone.

Effects of other drugs on the exposures of paliperidone are summarized in Figure 1. After oral administration of 20 mg/day of paroxetine (a potent CYP2D6 inhibitor), an increase in mean Cmax and AUC values at steady-state was observed (see Figure 1). Higher doses of paroxetine have not been studied. The clinical relevance is unknown. After oral administration, a decrease in mean Cmax and AUC values at steady state is expected when patients are treated with carbamazepine, a strong inducer of both CYP3A4 and P-gp [see Drug Interactions (7.1)]. This decrease is caused, to a substantial degree, by a 35% increase in renal clearance of paliperidone.

Figure 1: Effects of Other Drugs on Paliperidone Pharmacokinetics

Clinically meaningful pharmacokinetic interaction between paliperidone and valproate (including valproic acid and divalproex sodium) is not expected. Oral administration of divalproex sodium extended-release tablets (two 500 mg tablets once daily at steady-state) with oral paliperidone extended-release tablets resulted in an increase of approximately 50% in the Cmax and AUC of paliperidone.

After oral administration of paliperidone, the steady-state Cmax and AUC of divalproex sodium extended-release tablets were not affected in 13 patients stabilized on divalproex sodium extended- release tablets. In a clinical study, subjects on stable doses of divalproex sodium extended-release tablets had comparable valproate average plasma concentrations when oral paliperidone extended- release tablets 3-15 mg/day was added to their existing divalproex sodium extended-release tablets treatment [see Drug Interactions (7.2)].

In vitro studies indicate that CYP2D6 and CYP3A4 may be involved in paliperidone metabolism, however, there is no evidence in vivo that inhibitors of these enzymes significantly affect the metabolism of paliperidone; they contribute to only a small fraction of total body clearance. In vitro studies demonstrated that paliperidone is a substrate of P-glycoprotein (P-gp) [see Drug Interactions (7.2)].

In vitro studies in human liver microsomes demonstrated that paliperidone does not substantially inhibit the metabolism of drugs metabolized by cytochrome P450 isozymes, including CYP1A2, CYP2A6, CYP2C8/9/10, CYP2D6, CYP2E1, CYP3A4, and CYP3A5. Therefore, paliperidone is not expected to inhibit clearance of drugs that are metabolized by these metabolic pathways in a clinically relevant manner. Paliperidone is also not expected to have enzyme inducing properties.

Paliperidone is a weak inhibitor of P-gp at high concentrations. No in vivo data are available, and the clinical relevance is unknown.

Specific Populations

No pharmacokinetic studies have been performed with ERZOFRI in specific populations. The information is obtained from studies with oral paliperidone or is based on the population pharmacokinetic modeling of oral paliperidone and another PP1M. Exposures of paliperidone in specific populations (renal impairment, hepatic impairment and elderly) are summarized in Figure 2 [see Dosage and Administration (2.4) and Use in Specific Populations (8.6)].

After oral administration of paliperidone in patients with moderate hepatic impairment, the plasma concentrations of free paliperidone were similar to those of healthy subjects, although total paliperidone exposure decreased because of a decrease in protein binding. Paliperidone has not been studied in patients with severe hepatic impairment [see Use in Specific Populations (8.7)].

After oral administration of paliperidone in elderly subjects, the Cmax and AUC increased 1.2-fold compared to young subjects. However, there may be age-related decreases in creatinine clearance [see Dosage and Administration (2.4) and Use in Specific Populations (8.5)].

Figure 2 Effects of Intrinsic Factors on Paliperidone Pharmacokinetics

Based on in vitro studies utilizing human liver enzymes, paliperidone is not a substrate for CYP1A2; smoking should, therefore, not have an effect on the pharmacokinetics of paliperidone.

Slower absorption was observed in females in a population pharmacokinetic analysis. At apparent steady-state with PP1M, the trough concentrations were similar between males and females.

Lower Cmax was observed in overweight and obese subjects. At apparent steady-state PP1M, the trough concentrations were similar among normal, overweight, and obese subjects.

13 NONCLINICAL TOXICOLOGY

13.1 Carcinogenesis, Mutagenesis, Impairment of Fertility

Carcinogenesis

The carcinogenic potential of intramuscularly injected paliperidone palmitate was assessed in rats. There was an increase in mammary gland adenocarcinomas in female rats at 16, 47, and 94 mg/kg monthly injections, which are 0.6, 2, and 4 times, respectively, the MRHD of 234 mg of another once-a-month paliperidone palmitate extended-release injectable suspension based on body surface area (BSA). A no-effect dose was not established. Male rats showed an increase in mammary gland adenomas, fibroadenomas, and carcinomas at 2 and 4 times the MRHD based on BSA. A carcinogenicity study in mice has not been conducted with paliperidone palmitate.

Carcinogenicity studies with risperidone, which is extensively converted to paliperidone in rats, mice, and humans, were conducted in Swiss albino mice and Wistar rats. Risperidone was administered in the diet at daily doses of 0.63, 2.5, and 10 mg/kg for 18 months to mice and for 25 months to rats. A maximum tolerated dose was not achieved in male mice. There were statistically significant increases in pituitary gland adenomas, endocrine pancreas adenomas, and mammary gland adenocarcinomas. The no-effect dose for these tumors was less than or equal to the MRHD of risperidone based on BSA (see risperidone prescribing information). An increase in mammary, pituitary, and endocrine pancreas neoplasms has been found in rodents after chronic administration of other antipsychotic drugs and is considered to be mediated by prolonged dopamine D2 antagonism and hyperprolactinemia. The relevance of these tumor findings in rodents to human risk is unclear [see Warnings and Precautions (5.7)].

Mutagenesis

Paliperidone palmitate was not genotoxic in the in vitro Ames bacterial reverse mutation test or the mouse lymphoma assay. Paliperidone was not genotoxic in the in vitro Ames bacterial reverse mutation test, the mouse lymphoma assay, or the in vivo rat bone marrow micronucleus test.

Impairment of Fertility

No fertility studies were conducted with paliperidone palmitate.

Paliperidone did not affect fertility in treated female rats at oral doses of up to 2.5 mg/kg/day which is 2 times the MRHD based on BSA. However, pre- and post-implantation loss was increased, and the number of live embryos was slightly decreased, at 2.5 mg/kg, a dose that also caused slight maternal toxicity. These parameters were not affected at a dose of 0.63 mg/kg, which is half of the MRHD based on BSA.

Paliperidone did not affect fertility of treated male rats at oral doses of up to 2 times the MRHD of 12 mg/day based on BSA. However, studies to assess sperm count and sperm viability were not conducted with paliperidone. In a subchronic study in Beagle dogs with risperidone, which is extensively converted to paliperidone in dogs and humans, all doses tested (0.31 mg/kg - 5.0 mg/kg) resulted in decreases in serum testosterone and in sperm motility and concentration (0.6 to 10 times the MRHD of 16 mg/day for risperidone, based on BSA). Serum testosterone and sperm parameters partially recovered, and remained decreased after the last observation at two months after treatment was discontinued.

14 CLINICAL STUDIES

14.1 Schizophrenia

The efficacy of ERZOFRI for the treatment of schizophrenia in adults is based upon adequate and well-controlled studies of another once-a-month paliperidone palmitate extended-release injectable suspension (also referred to as "PP1M" in this section). The results of these adequate and well-controlled studies of another PP1M are presented below.

Short-Term Monotherapy (Studies 1, 2, 3, 4)

The efficacy of another PP1M in the acute treatment of schizophrenia was evaluated in four short-term (one 9-week and three 13-week) double-blind, randomized, placebo-controlled, fixed-dose studies of acutely relapsed adult inpatients who met DSM-IV criteria for schizophrenia. The fixed doses of PP1M in these studies were given on days 1, 8, and 36 in the 9-week study, and additionally on Day 64 of the 13-week studies, i.e., at a weekly interval for the initial two doses and then every 4 weeks for maintenance.

Efficacy was evaluated using the total score on the Positive and Negative Syndrome Scale (PANSS). The PANSS is a 30-item scale that measures positive symptoms of schizophrenia (7 items), negative symptoms of schizophrenia (7 items), and general psychopathology (16 items), each rated on a scale of 1 (absent) to 7 (extreme); total PANSS scores range from 30 to 210.

In Study 1 (PSY-3007), a 13-week study (n=636) comparing three fixed doses of PP1M (initial deltoid injection of 234 mg followed by 3 gluteal or deltoid doses of either 39 mg/4 weeks, 156 mg/4 weeks or 234 mg/4 weeks) to placebo, all three doses of PP1M were superior to placebo in improving the PANSS total score.

In Study 2 (PSY-3003), another 13-week study (n=349) comparing three fixed doses of PP1M (78 mg/4 weeks, 156 mg/4 weeks, and 234 mg/4 weeks) to placebo, only 156 mg/4 weeks of PP1M was superior to placebo in improving the PANSS total score.

In Study 3 (PSY-3004), a third 13-week study (n=513) comparing three fixed doses of PP1M (39 mg/4 weeks, 78 mg/4 weeks, and 156 mg/4 weeks) to placebo, all three doses of PP1M were superior to placebo in improving the PANSS total score.

In Study 4 (SCH-201), the 9-week study (n=197) comparing two fixed doses of PP1M (78 mg/4 weeks and 156 mg/4 weeks) to placebo, both doses of PP1M were superior to placebo in improving PANSS total score.

A summary of the mean baseline PANSS scores along with the mean changes from baseline in the four short-term acute schizophrenia studies are provided in Table 13.

Table 13: Schizophrenia Short-term Studies
Study Number | Treatment Group | Primary Efficacy Measure: PANSS Total Score
 |  | Mean Baseline Score (SD) | LS Mean Change from Baseline (SE) | Placebo-subtracted Difference [Difference (drug minus placebo) in least-squares mean change from baseline.] (95% CI)
Study 1 | Once-a-Month Paliperidone Palmitate Extended-Release Injectable Suspension (39 mg/4 weeks) [p<0.05 (Doses statistically significantly superior to placebo).] | 86.9 (11.99) | -11.2 (1.69) | -5.1 (-9.01, -1.10)
 | Once-a-Month Paliperidone Palmitate Extended-Release Injectable Suspension (156 mg/4 weeks) | 86.2 (10.77) | -14.8 (1.68) | -8.7 (-12.62, -4.78)
 | Once-a-Month Paliperidone Palmitate Extended-Release Injectable Suspension (234 mg/4 weeks) | 88.4 (11.70) | -15.9 (1.70) | -9.8 (-13.71, -5.85)
 | Placebo | 86.8 (10.31) | -6.1 (1.69) | --
Study 2 [Because an insufficient number of subjects received the 234 mg/4 weeks dose, results from this group are not included.] | Once-a-Month Paliperidone Palmitate Extended-Release Injectable Suspension (78 mg/4 weeks) | 89.9 (10.78) | -6.9 (2.50) | -3.5 (-8.73, 1.77)
 | Once-a-Month Paliperidone Palmitate Extended-Release Injectable Suspension (156 mg/4 weeks) | 90.1 (11.66) | -10.4 (2.47) | -6.9 (-12.12, -1.68)
 | Placebo | 92.4 (12.55) | -3.5 (2.15) | --
Study 3 | Once-a-Month Paliperidone Palmitate Extended-Release Injectable Suspension (39 mg/4 weeks) | 90.7 (12.25) | -19.8 (2.19) | -6.6 (-11.40, -1.73)
 | Once-a-Month Paliperidone Palmitate Extended-Release Injectable Suspension (78 mg/4 weeks) | 91.2 (12.02) | -19.2 (2.19) | -5.9 (-10.76, -1.07)
 | Once-a-Month Paliperidone Palmitate Extended-Release Injectable Suspension (156 mg/4 weeks) | 90.8 (11.70) | -22.5 (2.18) | -9.2 (-14.07, -4.43)
 | Placebo | 90.7 (12.22) | -13.3 (2.21) | --
Study 4 | Once-a-Month Paliperidone Palmitate Extended-Release Injectable Suspension (78 mg/4 weeks) | 88.0 (12.39) | -4.6 (2.43) | -11.2 (-16.85, -5.57)
 | Once-a-Month Paliperidone Palmitate Extended-Release Injectable Suspension (156 mg/4 weeks) | 85.2 (11.09) | -7.4 (2.45) | -14.0 (-19.51, -8.58)
 | Placebo | 87.8 (13.90) | 6.6 (2.45) | --
SD: standard deviation; SE: standard error; LS Mean: least-squares mean; CI: unadjusted confidence interval.

Maintenance Monotherapy Treatment (Study 5: PSY-3001)

The efficacy of another PP1M in maintaining symptomatic control in schizophrenia was established in a longer-term double-blind, placebo-controlled, flexible-dose study involving adult subjects who met DSM-IV criteria for schizophrenia. This study included a minimum 12-week, fixed-dose stabilization phase, and a randomized, placebo-controlled phase to observe for relapse. During the double-blind phase, patients were randomized to either the same dose of PP1M they received during the stabilization phase, i.e., 39 mg, 78 mg, or 156 mg administered every 4 weeks, or to placebo. A total of 410 stabilized patients were randomized to either PP1M or to placebo until they experienced a relapse of schizophrenia symptoms. Relapse was pre-defined as time to first emergence of one or more of the following: psychiatric hospitalization, ≥ 25% increase (if the baseline score was > 40) or a 10-point increase (if the baseline score was ≤ 40) in total PANSS score on two consecutive assessments, deliberate self-injury, violent behavior, suicidal/homicidal ideation, or a score of ≥ 5 (if the maximum baseline score was ≤ 3) or ≥ 6 (if the maximum baseline score was 4) on two consecutive assessments of the specific PANSS items. The primary efficacy variable was time to relapse. A pre-planned interim analysis showed a statistically significantly longer time to relapse in patients treated with PP1M compared to placebo, and the study was stopped early because maintenance of efficacy was demonstrated. Thirty-four percent (34%) of subjects in the placebo group and 10% of subjects in the PP1M group experienced a relapse event. There was a statistically significant difference between the treatment groups in favor of PP1M. A Kaplan-Meier plot of time to relapse by treatment group is shown in Figure 3. The time to relapse for subjects in the placebo group was statistically significantly shorter than for the PP1M group. An examination of population subgroups did not reveal any clinically significant differences in responsiveness on the basis of gender, age, or race.

Figure 3: Kaplan-Meier Plot of Cumulative Proportion of Subjects with Relapse Over Time (Schizophrenia Study 5)

* median time to relapse for placebo group is 163 days

Long-Term Comparative Monotherapy Treatment versus Oral Antipsychotic Therapy (Study 6: SCH-3006)

The efficacy of another PP1M in delaying time to treatment failure compared with selected oral antipsychotic medications was established in a long-term, randomized, flexible-dose study in subjects with schizophrenia and a history of incarceration. Subjects were screened for up to 14 days followed by a 15-month treatment phase during which they were observed for treatment failure.

The primary endpoint was time to first treatment failure. Treatment failure was defined as one of the following: arrest and/or incarceration; psychiatric hospitalization; discontinuation of antipsychotic treatment because of safety or tolerability; treatment supplementation with another antipsychotic because of inadequate efficacy; need for increase in level of psychiatric services to prevent an imminent psychiatric hospitalization; discontinuation of antipsychotic treatment because of inadequate efficacy; or suicide. Treatment failure was determined by an Event Monitoring Board (EMB) that was blinded to treatment assignment. A total of 444 subjects were randomly assigned to either PP1M (N = 226; median dose 156 mg) or one of up to seven pre-specified, flexibly-dosed, commonly prescribed oral antipsychotic medications (N = 218; aripiprazole, haloperidol, olanzapine, paliperidone, perphenazine, quetiapine, or risperidone). The selection of the oral antipsychotic medication was determined to be appropriate for the patient by the investigator. A statistically significantly longer time to first treatment failure was seen for PP1M compared with oral antipsychotic medications. The median time to treatment failure was 416 days and 226 days for PP1M and antipsychotic medications, respectively. A Kaplan-Meier plot of time to first treatment failure is shown in Figure 4. The frequencies of first treatment failure events by type are shown in Table 14. The time to first arrest and/or incarceration or psychiatric hospitalization was also statistically significantly longer for the PP1M group compared to the oral antipsychotic group.

Figure 4: Kaplan-Meier Plot of Time to First Treatment Failure in a Long-Term, Randomized, Flexible-Dose Study in Subjects with Schizophrenia and a History of Incarceration (Schizophrenia Study 6)

* Median time to first treatment failure: 416 days with once-a-month paliperidone palmitate extended-release injectable suspension; 226 days with oral antipsychotics

Table 14: Components of Composite Endpoint in a Long-Term, Randomized, Flexible-Dose Study in Subjects with Schizophrenia and a History of Incarceration (Schizophrenia Study 6)
Event Type | Once-a-Month Paliperidone Palmitate Extended-Release Injectable Suspension N=226 frequency (%) | Oral Antipsychotics N=218 frequency (%) | Hazard Ratio [Hazard ratio of once-a-month paliperidone palmitate extended-release injectable suspension to Oral Antipsychotics based on Cox regression model for time-to-event analysis. Note that the hazard ratio did not appear constant throughout the trial.] [95% CI]
First Treatment Failures | 90 (39.8%) | 117 (53.7%) | 0.70 [0.53, 0.92]
First Treatment Failure Component Events
- Arrest and/or incarceration | 48 (21.2%) | 64 (29.4%)
- Psychiatric hospitalization | 18 (8.0%) | 26 (11.9%)
- Discontinuation of antipsychotic treatment because of safety or tolerability | 15 (6.6%) | 8 (3.7%)
- Treatment supplementation with another antipsychotic because of inadequate efficacy | 5 (2.2%) | 6 (2.8%)
- Need for increase in level of psychiatric services to prevent an imminent psychiatric hospitalization | 3 (1.3%) | 4 (1.8%)
- Discontinuation of antipsychotic treatment because of inadequate efficacy | 1 (0.4%) | 9 (4.1%)
- Suicide | 0 | 0
Arrest and/or Incarceration or Psychiatric Hospitalization Events, regardless of whether they were first events [Analysis results, which incorporated relevant events collected after discontinuation for those who discontinued, were consistent with the results from the pre-specified analysis of this secondary endpoint.] | 76 (33.6%) | 98 (45.0%) | 0.70 [0.52, 0.94]

14.2 Schizoaffective Disorder

The efficacy of ERZOFRI for the treatment of schizoaffective disorder in adults as monotherapy and as an adjunct to mood stabilizers or antidepressants is based upon an adequate and well-controlled study of another PP1M. The results of the adequate and well-controlled study is presented below.

Maintenance Treatment – Monotherapy and as Adjunct to Mood Stabilizer or Antidepressant (SAff Study 1: SCA-3004)

The efficacy of PP1M in maintaining symptom control in schizoaffective disorder was established in a long-term double-blind, placebo-controlled, flexible-dose randomized-withdrawal study designed to delay relapse in adult subjects who met DSM-IV criteria for schizoaffective disorder, as confirmed by the Structured Clinical Interview for DSM-IV Disorders. The population included subjects with schizoaffective bipolar and depressive types. Subjects received PP1M either as monotherapy or as an adjunct to stable doses of antidepressant or mood stabilizers.

This study included a 13-week, open-label, flexible-dose (PP1M 78 mg, 117 mg, 156 mg, or 234 mg) lead-in period which enrolled a total of 667 subjects who had 1) acute exacerbation of psychotic symptoms; 2) score ≥4 on ≥3 PANSS items of delusions, conceptual disorganization, hallucinatory behavior, excitement, suspiciousness/persecution, hostility, uncooperativeness, tension, and poor impulse control; and 3) prominent mood symptoms ≥16 on the Young Mania Rating Scale (YMRS) and/or the Hamilton Rating Scale for Depression, 21-item version (HAM-D-21). Subjects were 19 to 66 years old (mean 39.5 years) and 53.5% were male. The mean scores at open-label enrollment of PANSS total was 85.8 (range 42 to 128), HAM-D- 21 was 20.4 (range 3 to 43), YMRS was 18.6 (range 0 to 50), and CGI-S-SCA was 4.4 (range 2 to 6).

After the 13-week open-label flexible-dose PP1M treatment, 432 subjects met stabilization criteria (PANSS total score ≤70, YMRS ≤12, and HAM-D-21 ≤12) and continued into the 12-week open-label fixed-dose stabilization period.

A total of 334 subjects who met stabilization criteria for 12 consecutive weeks were randomized (1:1) to continue the same dose of PP1M or to placebo in the 15-month, double- blind, maintenance period. For the 164 subjects who were randomized to PP1M, dose distribution was 78 mg (4.9%), 117 mg (9.8%), 156 mg (47.0%), and 234 mg (38.4%). The primary efficacy variable was time to relapse. Relapse was defined as the first occurrence of one or more of the following: 1) psychiatric hospitalization; 2) intervention employed to avert hospitalization; 3) clinically significant self-injury, suicidal or homicidal ideation or violent behavior; 4) a score of ≥6 (if the score was ≤4 at randomization) of any of the individual PANSS items: delusions, conceptual disorganization, hallucinatory behavior, excitement, suspiciousness/persecution, hostility, uncooperativeness, or poor impulse control; 5) on two consecutive assessments within 7 days: ≥ 25% increase (if the score at randomization was > 45) or ≥ 10-point increase (if the score at randomization was ≤ 45) in total PANSS score; a score of ≥ 5 (if the score was ≤ 3 at randomization) of any of the individual PANSS items: delusions, conceptual disorganization, hallucinatory behavior, excitement, suspiciousness/persecution, hostility, uncooperativeness, or poor impulse control; an increase of ≥ 2 points (if the score was 1 [not ill] to 3 [mildly ill] at randomization) or increase of ≥ 1 point (if the score was ≥ 4 [moderately ill or worse] at randomization) in CGI-S-SCA overall score.

There was a statistically significant difference in time to relapse between the treatment groups in favor of PP1M. A Kaplan-Meier plot of time to relapse by treatment group is shown in Figure 5.

Figure 5: Kaplan-Meier Plot of Cumulative Proportion of Subjects with Relapse Over Time (SAff Study 1)

Table 15 summarizes the number of subjects with relapse in the overall population, by subgroup (monotherapy versus adjunctive therapy), and by symptom type at the first occurrence of relapse.

Table 15: Summary of Relapse Rates (SAff Study 1).
 | Number (Percent) of Subjects Who Relapsed
 | Placebo | Once-a-Month Paliperidone Palmitate Extended-Release Injectable Suspension
 | N=170 | N=164
All Subjects | 57 (33.5%) | 25 (15.2%)
Monotherapy subset | N=73 24 (32.9%) | N=78 9 (11.5%)
Adjunct to Antidepressants or Mood Stabilizer subset | N=97 33 (34.0%) | N=86 16 (18.6%)
Psychotic Symptoms [8 subjects experienced a relapse without psychotic symptoms.] | 53 (31.2%) | 21 (12.8%)
Mood Symptoms [16 subjects experienced a relapse without any mood symptoms.]
Any Mood Symptoms | 48 (28.2%) | 18 (11.0%)
Manic | 16 (9.4%) | 5 (3.0%)
Depressive | 23 (13.5%) | 8 (4.9%)
Mixed | 9 (5.3%) | 5 (3.0%)

16 HOW SUPPLIED/STORAGE AND HANDLING

How Supplied

ERZOFRI® is provided as a single-use kit containing a single-dose prefilled syringe with a plunger stopper and tip cap. The kit also contains 2 safety needles (a 1 ½-inch 22 gauge safety needle and a 1-inch 23 gauge safety needle).

ERZOFRI is available as a white to off-white aqueous suspension in the following strengths:

39 mg/0.25 mL paliperidone palmitate kit | (NDC 72526-105-11)
78 mg/0.5 mL paliperidone palmitate kit | (NDC 72526-106-11)
117 mg/0.75 mL paliperidone palmitate kit | (NDC 72526-107-11)
156 mg/mL paliperidone palmitate kit | (NDC 72526-108-11)
234 mg/1.5 mL paliperidone palmitate kit | (NDC 72526-109-11)
351 mg/2.25 mL paliperidone palmitate kit | (NDC 72526-110-11)

Storage and Handling

Store at 20°C to 25°C (68°F to 77°F); excursions permitted between 15°C and 30°C (59°F to 86°F) [see USP Controlled Room Temperature]. Do not mix with any other product or diluent.

17 PATIENT COUNSELING INFORMATION

Advise the patient to read the FDA-approved patient labeling (Patient Information).

Neuroleptic Malignant Syndrome (NMS)

Counsel patients about a potentially fatal adverse reaction, Neuroleptic Malignant Syndrome (NMS), that has been reported in association with administration of antipsychotic drugs. Advise patients, family members, or caregivers to contact their healthcare provider or report to the emergency room if they experience signs and symptoms of NMS, including hyperpyrexia, muscle rigidity, altered mental status including delirium, and evidence of autonomic instability (irregular pulse or blood pressure, tachycardia, diaphoresis, and cardiac dysrhythmia) [see Warnings and Precautions (5.3)].

Tardive Dyskinesia

Counsel patients on the signs and symptoms of tardive dyskinesia and to contact their healthcare provider if these abnormal movements occur [see Warnings and Precautions (5.5)].

Metabolic Changes

Educate patients about the risk of metabolic changes, how to recognize symptoms of hyperglycemia and diabetes mellitus, and the need for specific monitoring, including blood glucose, lipids, and weight [see Warnings and Precautions (5.6)].

Orthostatic Hypotension

Educate patients about the risk of orthostatic hypotension and syncope, particularly at the time of initiating treatment, re-initiating treatment, or increasing the dose [see Warnings and Precautions (5.7)].

Leukopenia/Neutropenia

Advise patients with a pre-existing low WBC or a history of drug-induced leukopenia/neutropenia that they should have their CBC monitored while taking ERZOFRI [see Warnings and Precautions (5.9)].

Hyperprolactinemia

Counsel patients on signs and symptoms of hyperprolactinemia that may be associated with chronic use of ERZOFRI. Advise them to seek medical attention if they experience any of the following: amenorrhea or galactorrhea in females, erectile dysfunction or gynecomastia in males [see Warnings and Precautions (5.10)].

Potential for Cognitive and Motor Impairment

As ERZOFRI has the potential to impair judgement, thinking or motor skills, caution patients about operating hazardous machinery, including motor vehicles, until they are reasonably certain that ERZOFRI therapy does not affect them adversely [see Warnings and Precautions (5.11)].

Priapism

Advise patients of the possibility of painful or prolonged penile erections (priapism). Instruct the patient to seek immediate medical attention in the event of priapism [see Warnings and Precautions (5.14)].

Heat Exposure and Dehydration

Counsel patients regarding appropriate care in avoiding overheating and dehydration [see Warnings and Precautions (5.15)].

Concomitant Medication

Advise patients to inform their healthcare providers if they are taking, or plan to take any prescription or over-the-counter medications because there is a potential for clinically significant interactions [see Drug Interactions (7)].

Alcohol

Advise patients to avoid alcohol during treatment with ERZOFRI [see Drug Interactions (7.1)].

Pregnancy

Advise patients to notify their healthcare provider if they become pregnant or intend to become pregnant during treatment with ERZOFRI. Advise patients that ERZOFRI may cause extrapyramidal and/or withdrawal symptoms in a neonate. Advise patients that there is a pregnancy registry that monitors pregnancy outcomes in women exposed to ERZOFRI during pregnancy [see Use in Specific Populations (8.1)].

Lactation

Advise breastfeeding women using ERZOFRI to monitor infants for somnolence, failure to thrive, jitteriness, and extrapyramidal symptoms (tremors and abnormal muscle movements) and to seek medical care if they notice these signs [see Use in Specific Populations (8.2)].

Infertility

Advise females of reproductive potential that ERZOFRI may impair fertility due to an increase in serum prolactin levels. The effects on fertility are reversible [see Use in Specific Populations (8.3)].

ERZOFRI® (paliperidone palmitate) extended-release injectable suspension

Product of China.

Manufactured by:

Shandong Luye Pharmaceutical Co., Ltd.
No.15 Chuangye Road
Yantai, Shandong Province, China 264003

Manufactured for:
Luye Innomind Pharma Shijiazhuang Co., Ltd.
Shijiazhuang, Hebei Province, China 050000

For patent information: www.luyeusa.com/patents

© 2024 Luye Innomind Pharma Shijiazhuang Co., Ltd.

PATIENT INFORMATION
ERZOFRI® (er-ZOH-free)
(paliperidone palmitate)
extended-release injectable suspension

What is the most important information I should know about ERZOFRI?

ERZOFRI may cause serious side effects, including:

- Increased risk of death in elderly people with dementia-related psychosis. ERZOFRI increases the risk of death in elderly people who have lost touch with reality (psychosis) due to confusion and memory loss (dementia). ERZOFRI is not for the treatment of people with dementia-related psychosis.

What is ERZOFRI?

ERZOFRI is a prescription medicine given by injection by a healthcare provider and used to treat:

- schizophrenia in adults
- schizoaffective disorder in adults either alone or with other medicines such as mood stabilizers or antidepressants

It is not known if ERZOFRI is safe and effective in children.

Who should not receive ERZOFRI?

Do not receive ERZOFRI if you are allergic to paliperidone, risperidone, or any of the ingredients in ERZOFRI. See the end of this Patient Information leaflet for a complete list of ingredients in ERZOFRI.

Before receiving ERZOFRI, tell your healthcare provider about all your medical conditions, including if you:

- have never taken paliperidone or risperidone before
- have had Neuroleptic Malignant Syndrome (NMS)
- have or had heart problems, including a heart attack, heart failure, abnormal heart rhythm, or long QT syndrome
- have or had low levels of potassium or magnesium in your blood
- have or had uncontrolled movements of your tongue, face, mouth, or jaw (tardive dyskinesia)
- have or had kidney or liver problems
- have or had high blood sugar, diabetes or have a family history of diabetes
- have or had high levels of total cholesterol, LDL cholesterol, or triglycerides, or low levels of HDL cholesterol
- have Parkinson's disease or a type of dementia called Lewy Body Dementia
- have or had problems with dizziness or fainting or are being treated for high blood pressure
- have or had a low white blood cell count
- have or had seizures or epilepsy
- are pregnant or plan to become pregnant. It is not known if ERZOFRI will harm your unborn baby.
  - If you become pregnant during treatment with ERZOFRI, talk to your healthcare provider about registering with the National Pregnancy Registry for Atypical Antipsychotics. You can register by calling 1-866-961-2388 or visit http://womensmentalhealth.org/clinical-and-research-programs/pregnancyregistry/.
  - Babies born to women who are treated with ERZOFRI during their third trimester of pregnancy may experience symptoms such as tremors, irritability, excessive sleepiness, eye twitching, muscle spasms, decreased appetite, difficulty breathing, or abnormal movement of arms and legs. Let your healthcare provider know if these symptoms occur.
- are breastfeeding or plan to breastfeed. ERZOFRI can pass into your breast milk.
  - Talk to your healthcare provider about the best way to feed your baby if you receive ERZOFRI.

Tell your healthcare provider about all the medicines you take, including prescription and over-the-counter medicines, vitamins, and herbal supplements. ERZOFRI and certain other medicines may affect each other causing possible serious side effects or affect the way each other works. Know the medicines you take. Keep a list of them to show to your healthcare provider or pharmacist when you get a new medicine.

How will I receive ERZOFRI?

- Follow your ERZOFRI treatment schedule exactly as your healthcare provider tells you to.
- Your healthcare provider will tell you how much ERZOFRI you will receive and when you will receive it.
- ERZOFRI is given as an injection by your healthcare provider into the muscle (intramuscularly) of your arm or your buttocks 1 time every month. Your first ERZOFRI injection will be in your arm.
- If you miss a dose of ERZOFRI, call your healthcare provider right away to schedule your next injection.

What should I avoid while receiving ERZOFRI?

- Do not drive, operate heavy machinery, or do other dangerous activities until you know how ERZOFRI affects you. ERZOFRI may affect your ability to make decisions, think clearly, or react quickly.
- Avoid getting too hot or becoming dehydrated.

- Do not exercise too much.
- In hot weather, stay inside in a cool place if possible.
- Stay out of the sun.

- Do not wear too much clothing or heavy clothing.
- Drink plenty of water.

- Avoid alcohol during treatment with ERZOFRI.

What are the possible side effects of ERZOFRI?

ERZOFRI may cause serious side effects, including:

- See "What is the most important information I should know about ERZOFRI"
- Cardiovascular problems (including stroke) in elderly people with dementia-related psychosis that can lead to death.
- Neuroleptic Malignant Syndrome (NMS), a serious condition that can lead to death. Call your healthcare provider right away or go to your nearest emergency room right away if you get any of the following signs or symptoms:

- high fever
- stiff muscles
- confusion

- sweating
- changes in your breathing, pulse, heart rate, or blood pressure

- Problems with your heartbeat. These heart problems can cause death. Call your healthcare provider right away if you get any of these symptoms:
  - passing out or feeling like you will pass out
  - dizziness
  - feeling as if your heart is pounding or missing beats
- Uncontrolled body movements (tardive dyskinesia). ERZOFRI may cause movements that you cannot control in your face, tongue, or other body parts. Tardive dyskinesia may not go away, even if you stop taking ERZOFRI. Tardive dyskinesia may also start after you stop taking ERZOFRI.
- Problems with your metabolism such as:
  - High blood sugar (hyperglycemia) and diabetes. Increases in blood sugar can happen in some people who are treated with ERZOFRI. Extremely high blood sugar can lead to coma or death. If you have diabetes or risk factors for diabetes such as being overweight, or a family history of diabetes, your healthcare provider should check your blood sugar before you start treatment and during your treatment with ERZOFRI.
    Call your healthcare provider if you get any of these symptoms of high blood sugar during treatment with ERZOFRI:

- feel very thirsty
- feel very hungry
- feel sick to your stomach

- need to urinate more than usual
- feel weak or tired
- feel confused, or your breath smells fruity

- Increased fat levels (cholesterol and triglycerides) in your blood. Your healthcare provider may check your cholesterol and triglyceride levels during treatment with ERZOFRI.
- Weight gain. You and your healthcare provider should check your weight regularly during treatment with ERZOFRI.

- Decreased blood pressure (orthostatic hypotension) and fainting. You may feel lightheaded or faint when you rise too quickly from a sitting or lying position.
- Falls. ERZOFRI may make you sleepy or dizzy, may cause a decrease in your blood pressure when changing position (orthostatic hypotension), and can slow your thinking and motor skills which may lead to falls that can cause fractures or other injuries.
- Low white blood cell counts. Your healthcare provider may do blood tests during treatment with ERZOFRI.
- Increased prolactin levels in your blood (hyperprolactinemia). ERZOFRI may cause a rise in the blood levels of a hormone called prolactin that may cause side effects including missed menstrual periods, a reversible reduction in fertility in females who are able to become pregnant, leakage of milk from the breasts, development of breasts in men, or problems with erection.
- Sleepiness, drowsiness, feeling tired, difficulty thinking and doing normal activities. See "What should I avoid while receiving ERZOFRI?"
- Seizures (convulsions).
- Difficulty swallowing that can cause food or liquid to get into your lungs.
- Prolonged or painful erection lasting more than 4 hours (priapism). Call your healthcare provider or go to your nearest emergency room right away if you have an erection that lasts more than 4 hours.
- Problems with control of your body temperature so that you feel too warm. See "What should I avoid while receiving ERZOFRI?"

The most common side effects of ERZOFRI include:

- injection site reactions
- sleepiness or drowsiness
- dizziness

- feeling restless or like you need to move
- abnormal muscle movements including tremor (shaking), shuffling, uncontrolled involuntary movements, and abnormal movements of your eyes

Tell your healthcare provider if you have any side effect that bothers you or does not go away.

These are not all of the possible side effects of ERZOFRI. Call your doctor for medical advice about side effects. You may report side effects to FDA at 1-800-FDA-1088.

General information about the safe and effective use of ERZOFRI.

Medicines are sometimes prescribed for purposes other than those listed in a Patient Information leaflet. You can ask your pharmacist or healthcare provider for information about ERZOFRI that is written for health professionals.

What are the ingredients in ERZOFRI?

Active ingredient: paliperidone palmitate

Inactive ingredients: citric acid monohydrate, dibasic sodium phosphate anhydrous, monobasic sodium phosphate monohydrate, polyethylene glycol 4000, polysorbate 20, sodium hydroxide, and water for injection.

Manufactured by: Shandong Luye Pharmaceutical Co., Ltd., No.15 Chuangye Road, Yantai, Shandong Province, China 264003

Manufactured for: Luye Innomind Pharma Shijiazhuang Co., Ltd., Shijiazhuang, Hebei Province, China 050000
For more information call 1-800-548-9765.

This Patient Information has been approved by the U.S. Food and Drug Administration.

Revised: 3/2025

PRINCIPAL DISPLAY PANEL - 39 mg/0.25 mL Syringe Kit

NDC 72526-105-11
Rx Only

Erzofri®
(paliperidone palmitate)
extended-release injectable suspension

39 mg/0.25 mL

For Single Use Only.
Use entire contents of syringe.

FOR INTRAMUSCULAR INJECTION ONLY.
Shake before using. Each injection must be administered by a healthcare professional.

PRINCIPAL DISPLAY PANEL - 78 mg/0.5 mL Syringe Kit

NDC 72526-106-11
Rx Only

Erzofri®
(paliperidone palmitate)
extended-release injectable suspension

78 mg/0.5 mL

For Single Use Only.
Use entire contents of syringe.

FOR INTRAMUSCULAR INJECTION ONLY.
Shake before using. Each injection must be administered by a healthcare professional.

PRINCIPAL DISPLAY PANEL - 117 mg/0.75 mL Syringe Kit

NDC 72526-107-11
Rx Only

Erzofri®
(paliperidone palmitate)
extended-release injectable suspension

117 mg/0.75 mL

For Single Use Only.
Use entire contents of syringe.

FOR INTRAMUSCULAR INJECTION ONLY.
Shake before using. Each injection must be administered by a healthcare professional.

PRINCIPAL DISPLAY PANEL - 156 mg/mL Syringe Kit

NDC 72526-108-11
Rx Only

Erzofri®
(paliperidone palmitate)
extended-release injectable suspension

156 mg/mL

For Single Use Only.
Use entire contents of syringe.

FOR INTRAMUSCULAR INJECTION ONLY.
Shake before using. Each injection must be administered by a healthcare professional.

PRINCIPAL DISPLAY PANEL - 234 mg/1.5 mL Syringe Kit

NDC 72526-109-11
Rx Only

Erzofri®
(paliperidone palmitate)
extended-release injectable suspension

234 mg/1.5 mL

For Single Use Only.
Use entire contents of syringe.

FOR INTRAMUSCULAR INJECTION ONLY.
Shake before using. Each injection must be administered by a healthcare professional.

PRINCIPAL DISPLAY PANEL - 351 mg/2.25 mL Syringe Kit

NDC 72526-110-11
Rx Only

Erzofri®
(paliperidone palmitate)
extended-release injectable suspension

351 mg/2.25 mL

For Single Use Only.
Use entire contents of syringe.

FOR INTRAMUSCULAR INJECTION ONLY.
Shake before using. Each injection must be administered by a healthcare professional.